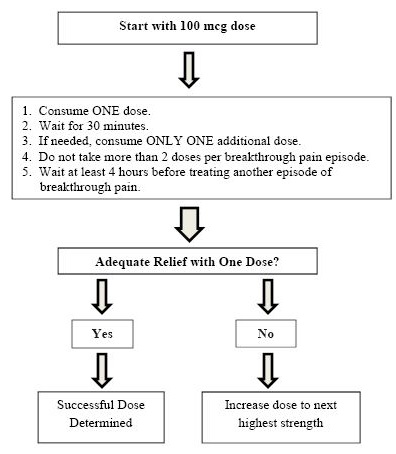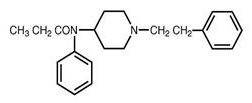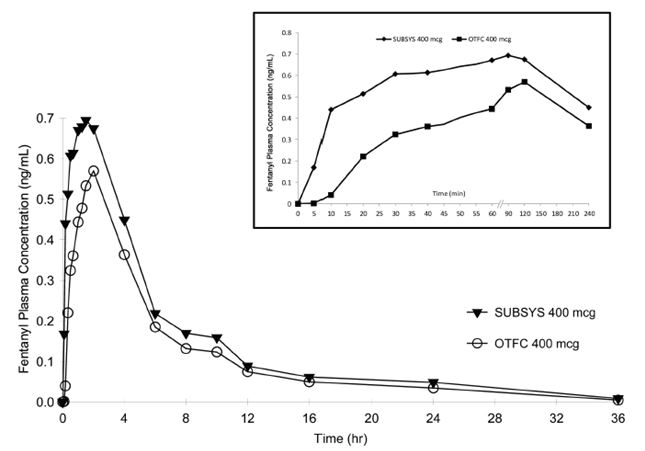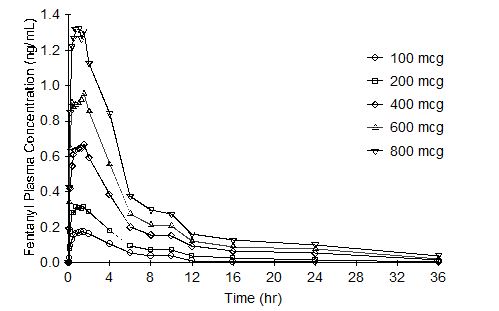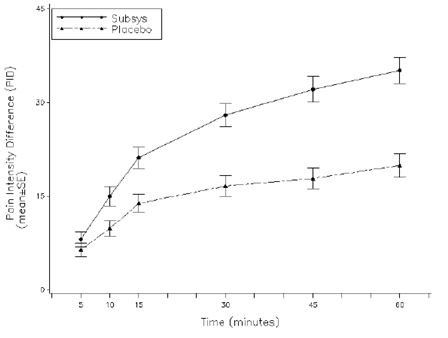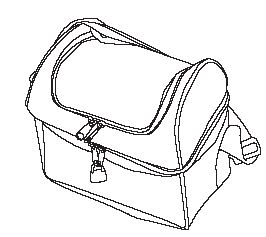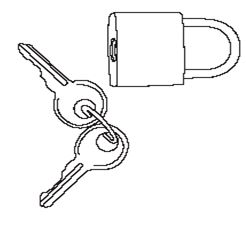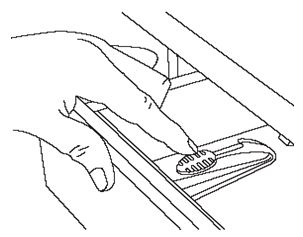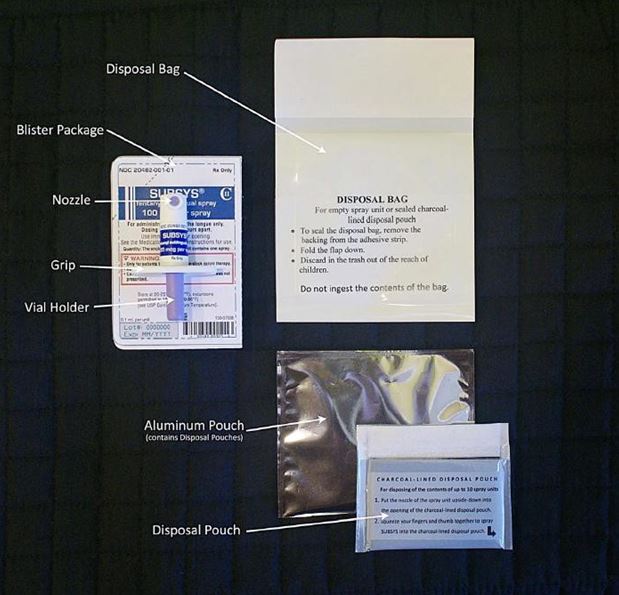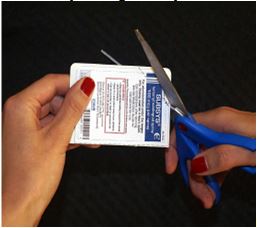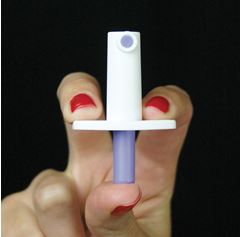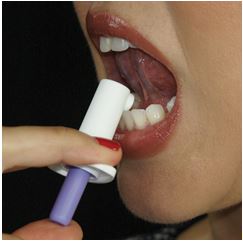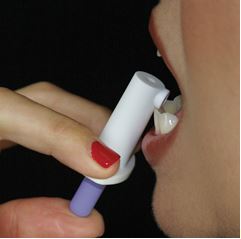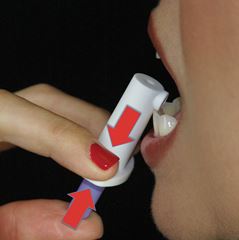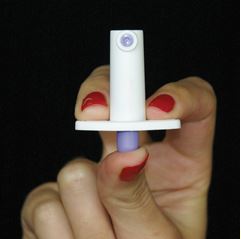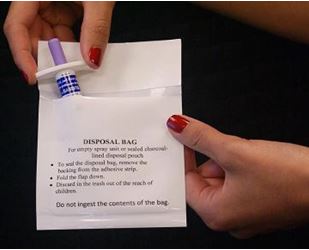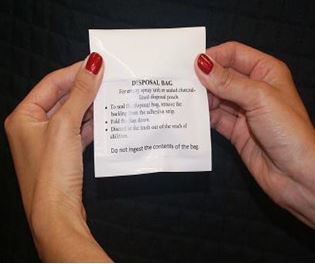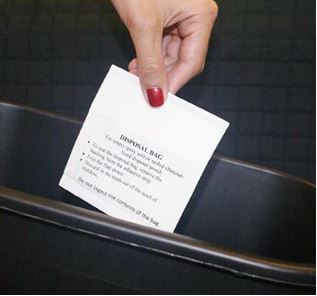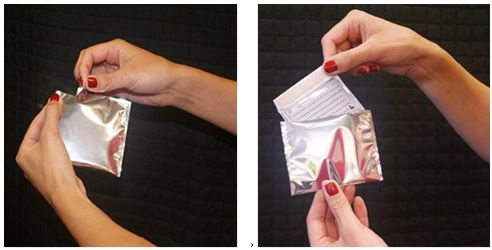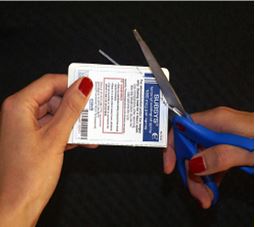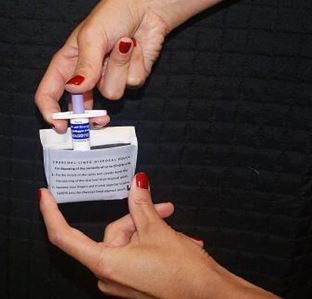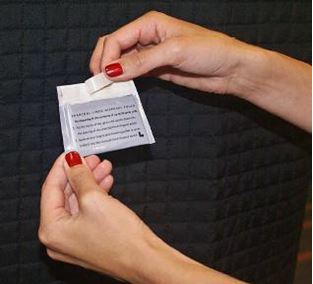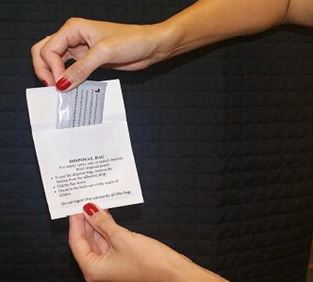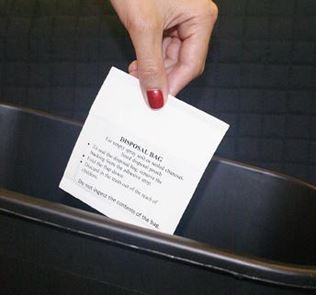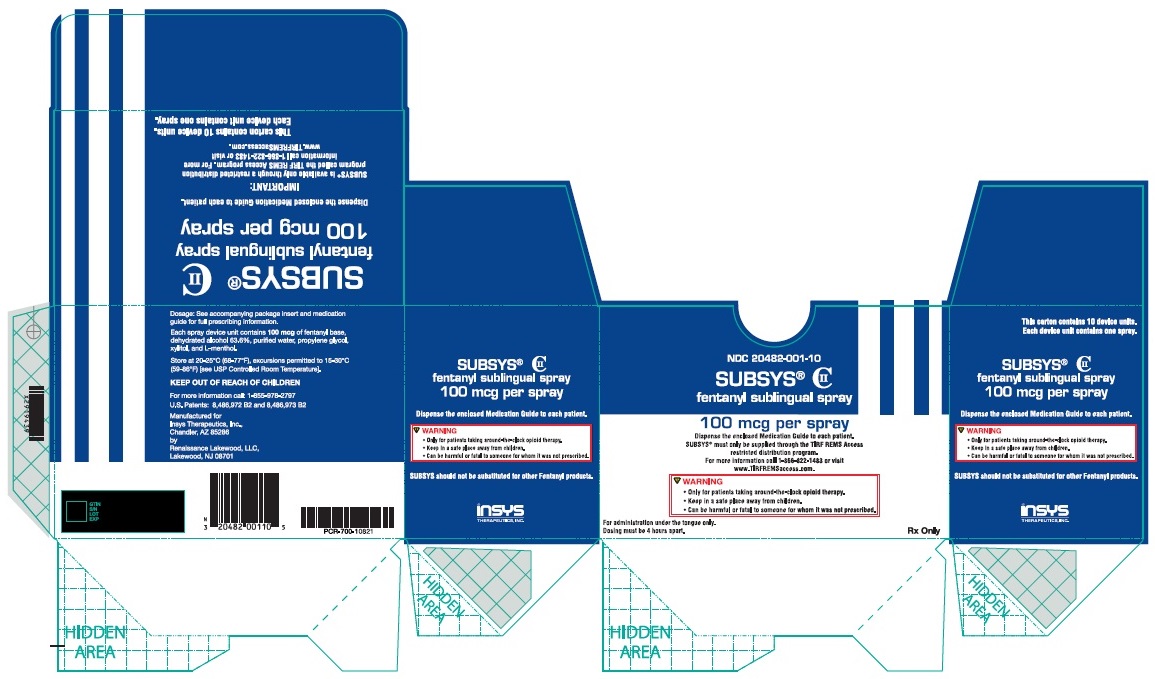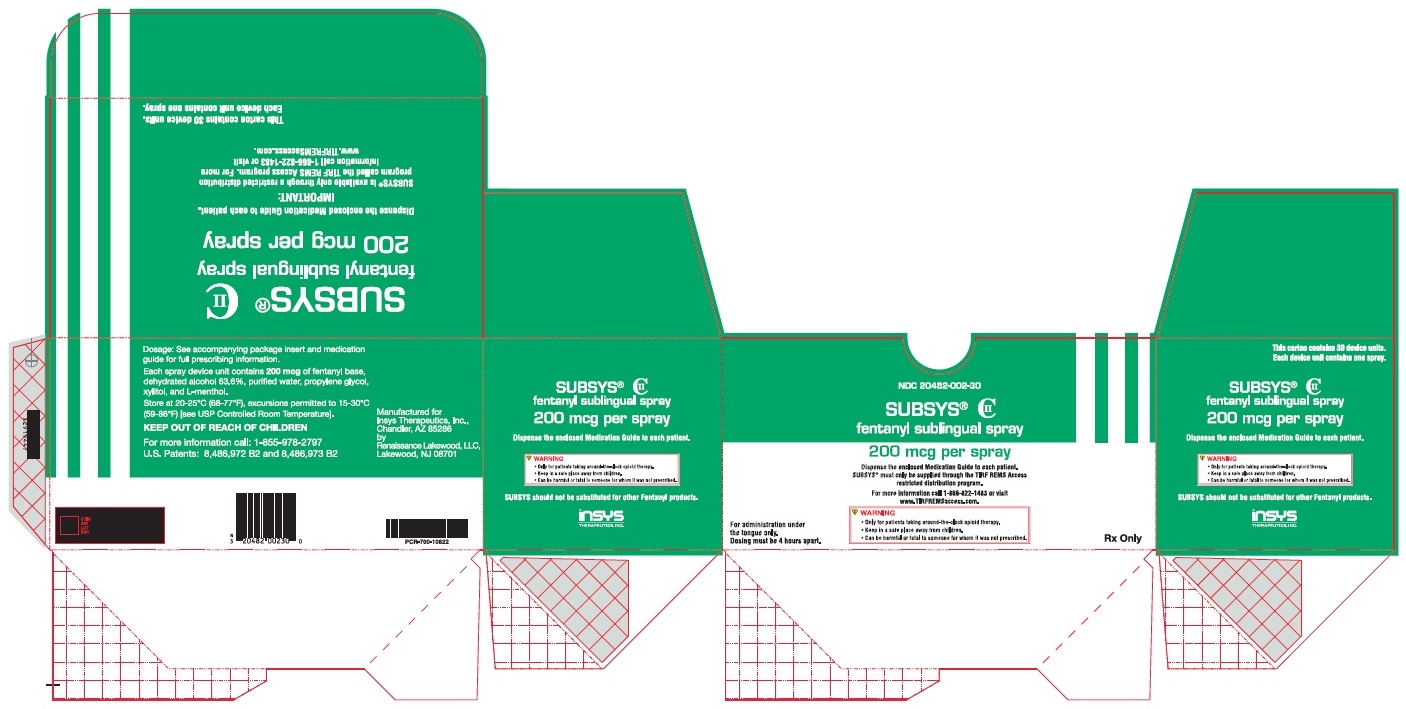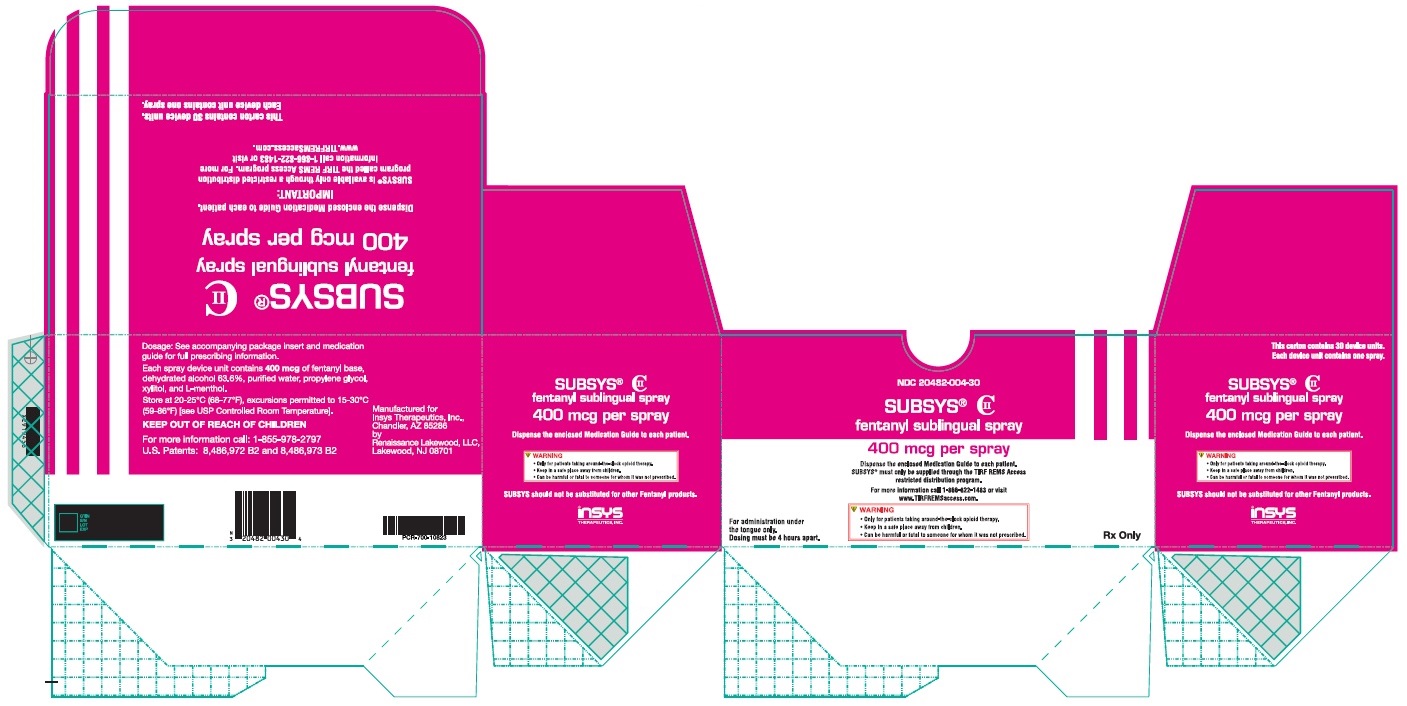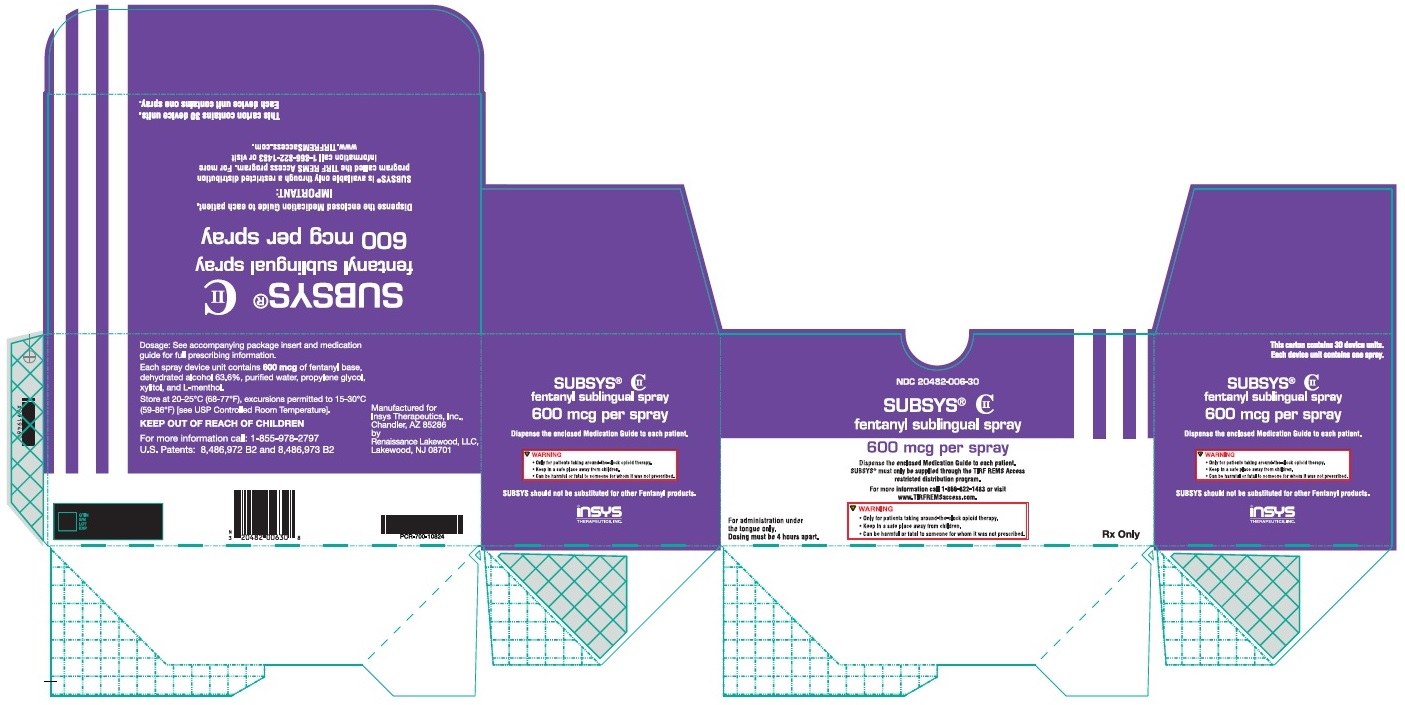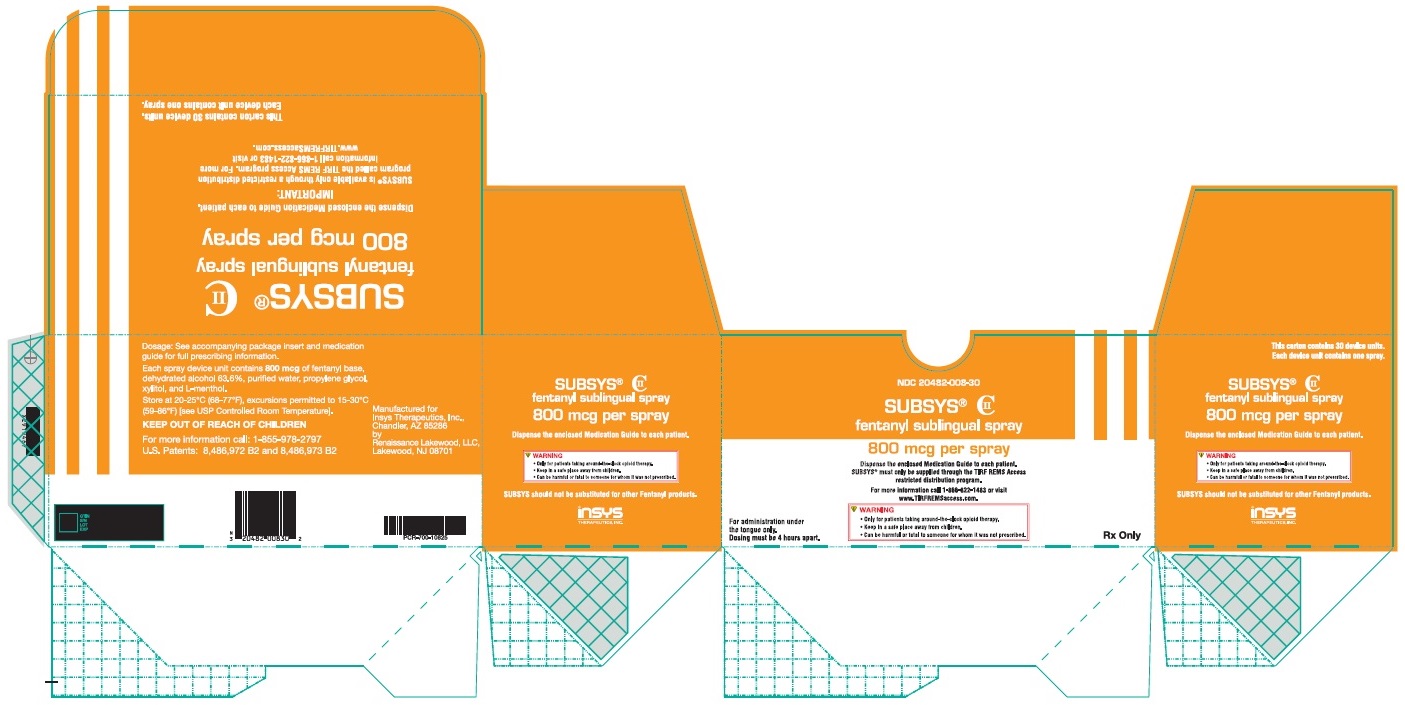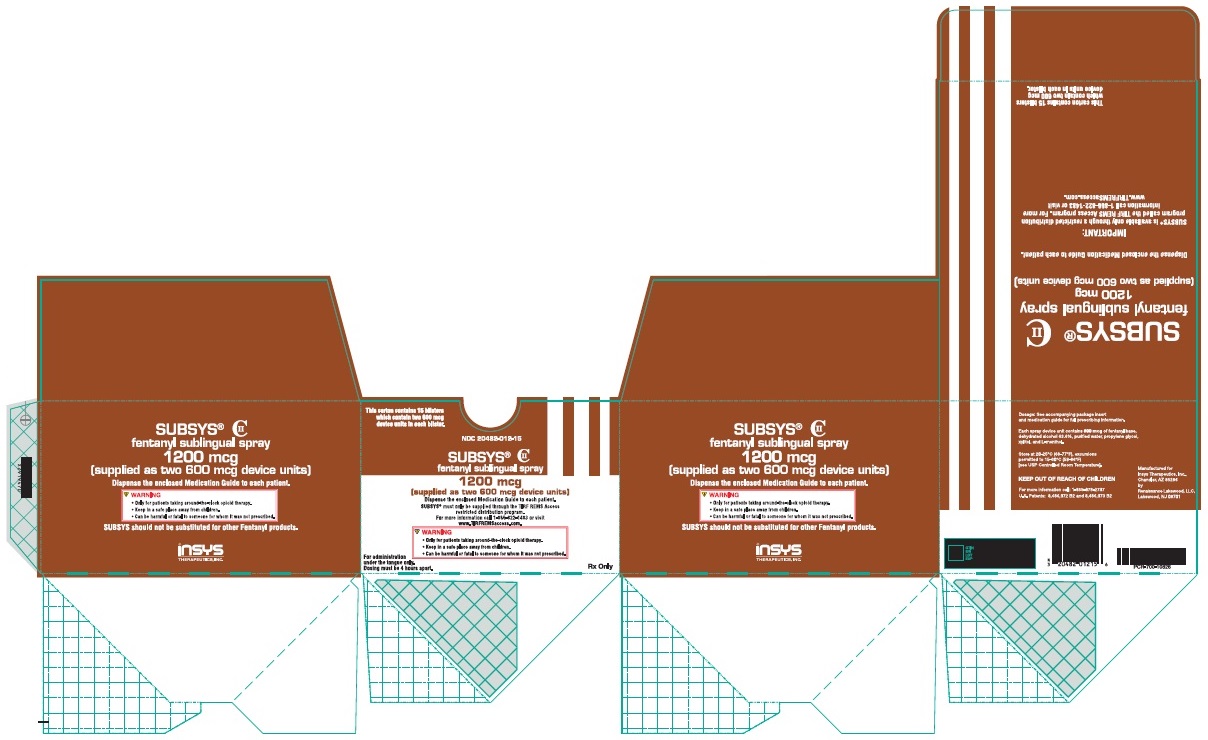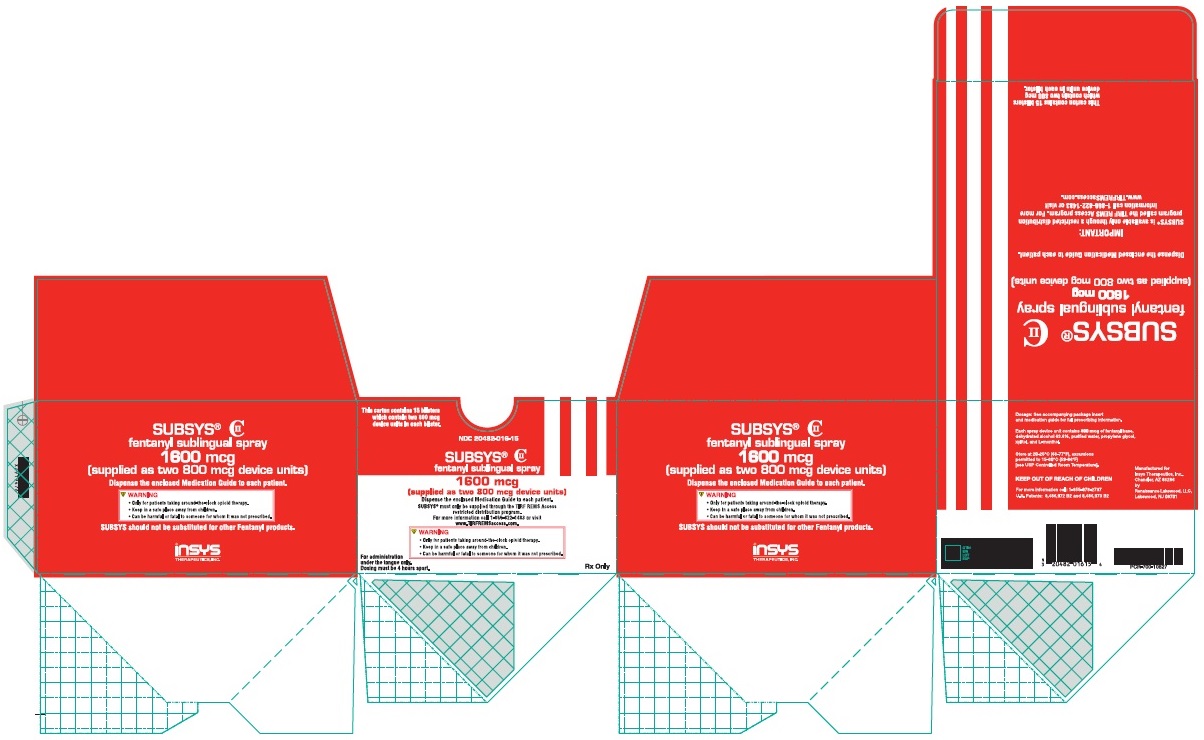 DRUG LABEL: SUBSYS
NDC: 20482-001 | Form: SPRAY
Manufacturer: Insys Therapeutics, Inc.
Category: prescription | Type: HUMAN PRESCRIPTION DRUG LABEL
Date: 20210504
DEA Schedule: CII

ACTIVE INGREDIENTS: FENTANYL 0.1 mg/1 1

HIGHLIGHTS OF PRESCRIBING INFORMATION

These highlights do not include all the information needed to use SUBSYS safely and effectively. See full prescribing information for SUBSYS.
SUBSYS®(fentanyl sublingual spray), CII
Initial U.S. Approval: 1968

RECENT MAJOR CHANGES

Boxed Warning | 03/2021
Dosage and Administration (2.2) | 03/2021
Warnings and Precautions (5.1, 5.4, 5.6, 5.7) | 03/2021

WARNING: LIFE THREATENTING RESPIRATORY DEPRESSION; ACCIDENTAL EXPOSURE, CYTOCHROME P450 3A4 INTERACTION; RISKS FROM CONCOMITANT USE WITH BENZODIAZEPINES OR OTHER CNS DEPRESSANTS; RISK OF MEDICATION ERRORS; ADDICTION, ABUSE, AND MISUSE; REMS; and NEONATAL OPIOID WITHDRAWAL SYNDROME

WARNING: LIFE-THREATENING RESPIRATORY DEPRESSION, ACCIDENTAL INGESTION; CYTOCHROME P450 3A4 INTERACTION; RISKS FROM CONCOMITANT USE WITH BENZODIAZEPINES OR OTHER CNS DEPRESSANTS; RISK OF MEDICATION ERRORS; ADDICTION, ABUSE, AND MISUSE; REMS; and NEONATAL OPIOID WITHDRAWAL SYNDROME
See full prescribing information for complete boxed warning.

- Serious, life-threatening, and/or fatal respiratory depression has occurred. Monitor closely, especially upon initiation or following a dose increase. Due to the risk of fatal respiratory depression, SUBSYS is contraindicated in opioid non-tolerant patients (1) and in management of acute or postoperative pain, including headache/migraines. (5.1)
- Accidental ingestion of SUBSYS, especially by children, can result in a fatal overdose of fentanyl. Keep out of reach of children. Ensure proper storage and disposal. (5.2)
- Concomitant use with CYP3A4 inhibitors (or discontinuation of CYP3A4 inducers) can result in a fatal overdose of fentanyl. (5.3, 7, 12.2)
- Concomitant use of opioids with benzodiazepines or other central nervous system (CNS) depressants, including alcohol, may result in profound sedation, respiratory depression, coma, and death. Reserve concomitant prescribing for use in patients for whom alternative treatment options are inadequate; limit dosages and durations to the minimum required and follow patients for signs and symptoms of respiratory depression and sedation. (5.4, 7)
- When prescribing, do not convert patients on a mcg per mcg basis from any other oral transmucosal fentanyl product to SUBSYS. (2.3, 5.5)
- When dispensing, do not substitute with any other fentanyl products. (5.5)
- SUBSYS exposes users to risks of addiction, abuse, and misuse, which can lead to overdose and death. Assess patient’s risk before prescribing and monitor regularly for these behaviors and conditions. (5.6)
- SUBSYS is available only through a restricted program called the TIRF REMS Access program. Outpatients, healthcare professionals who prescribe to outpatients, pharmacies, and distributors are required to enroll in the program. (5.7)
- Prolonged use of SUBSYS during pregnancy can result in neonatal opioid withdrawal syndrome, which may be life-threatening if not recognized and treated. If prolonged opioid use is required in a pregnant woman, advise the patient of the risk of neonatal opioid withdrawal syndrome and ensure that appropriate treatment will be available. (5.8)

1 INDICATIONS AND USAGE

SUBSYS is an opioid agonist indicated for the management of breakthrough pain in cancer patients 18 years of age and older who are already receiving and who are tolerant to around-the-clock opioid therapy for their underlying persistent cancer pain. (1)

Patients considered opioid tolerant are those who are taking, for one week or longer, around-the-clock medicine consisting of at least 60 mg of oral morphine per day, at least 25 mcg of transdermal fentanyl per hour, at least 30 mg of oral oxycodone per day, at least 8 mg of oral hydromorphone per day, at least 25 mg oral oxymorphone per day, at least 60 mg oral hydrocodone per day, or an equianalgesic dose of another opioid daily for a week or longer. Patients must remain on around-the-clock opioids when taking SUBSYS.

Limitations of Use (1):

- Not for use in opioid non-tolerant patients.
- Not for use in the management of acute or postoperative pain, including headache/migraine, dental pain, or in the emergency room.
- As a part of the Transmucosal Immediate-Release Fentanyl (TIRF) REMS, SUBSYS may be dispensed by outpatient pharmacies only to outpatients enrolled in the program (5.7) . For inpatient administration of SUBSYS, patient and prescriber enrollment are not required.

2 DOSAGE AND ADMINISTRATION

- Patients must require and use around-the-clock opioids when taking SUBSYS. (1)
- Use the lowest effective dose for the shortest duration consistent with individual patient treatment goals (2.1)
- Individualize dosing based on the severity of pain, patient response, prior analgesic experience, and risk factors for addiction, abuse, and misuse. (2.1)
- Initiate treatment with 100 mcg except patients already using Actiq. (2.3)
- Individually titrate to a tolerable dose that provides adequate analgesia using a single SUBSYS dose per breakthrough cancer pain episode. (2.5)
- No more than two doses can be taken per breakthrough pain episode. (2.4)
- Wait at least 4 hours before treating another episode of breakthrough pain with SUBSYS. (2.5)
- Limit consumption to four or fewer doses per day once successful dose is found. (2.5)
- When opioid therapy is no longer required, consider discontinuing SUBSYS along with a gradual downward titration of other opioids to minimize possible withdrawal effects. (2.6).

3 DOSAGE FORMS AND STRENGTHS

Sublingual spray in 100 mcg, 200 mcg, 400 mcg, 600 mcg, 800 mcg dosage strengths. (3)

4 CONTRAINDICATIONS

- Opioid non-tolerant patients. (4)
- Management of acute or postoperative pain including headache/migraine and dental pain, or in emergency department. (4)
- Acute or severe bronchial asthma in an unmonitored setting or in absence of resuscitative equipment. (4)
- Known or suspected gastrointestinal obstruction, including paralytic ileus. (4)
- Known hypersensitivity to fentanyl, or components of SUBSYS. (4)

5 WARNINGS AND PRECAUTIONS

- Life-Threatening Respiratory Depression in Patients with Chronic Pulmonary Disease or in Elderly, Cachectic, or Debilitated Patients: Monitor closely, particularly during initiation and titration. (5.9)
- Serotonin Syndrome: Potentially life-threatening condition could result from concomitant serotonergic drug administration. Discontinue SUBSYS if serotonin syndrome is suspected. (5.10)
- Adrenal Insufficiency: If diagnosed, treat with physiologic replacement of corticosteroids, and wean patient off of the opioid. (5.11)
- Severe Hypotension: Monitor during dosage initiation and titration. Avoid use of SUBSYS in patients with circulatory shock. (5.12)
- Risks of Use in Patients with Increased Intracranial Pressure, Brain Tumors, Head Injury, or Impaired Consciousness: Monitor for sedation and respiratory depression. Avoid use of SUBSYS in patients with impaired consciousness or coma. (5.13)

6 ADVERSE REACTIONS

Most common adverse reactions during treatment (incidence ≥ 5%): vomiting, nausea, constipation, dyspnea, and somnolence. (6)

To report SUSPECTED ADVERSE REACTIONS, contact West Therapeutic Development, LLC., at 1-844-452-9263 or FDA at 1-800-FDA-1088 or www.fda.gov/medwatch.

7 DRUG INTERACTIONS

- Mixed Agonist/Antagonist and Partial Agonist Opioid Analgesics: Avoid use with SUBSYS because they may reduce analgesic effect of SUBSYS or precipitate withdrawal symptoms. (7)

8 USE IN SPECIFIC POPULATIONS

- Pregnancy: May cause fetal harm (8.1)
- Lactation: Not Recommended.
- Renal and Hepatic Impairment: Administer SUBSYS with caution. (8.6)

FULL PRESCRIBING INFORMATION

WARNING: LIFE THREATENTING RESPIRATORY DEPRESSION; ACCIDENTAL EXPOSURE, CYTOCHROME P450 3A4 INTERACTION; RISKS FROM CONCOMITANT USE WITH BENZODIAZEPINES OR OTHER CNS DEPRESSANTS; RISK OF MEDICATION ERRORS; ADDICTION, ABUSE, AND MISUSE; REMS; and NEONATAL OPIOID WITHDRAWAL SYNDROME

Life-Threatening Respiratory Depression
Serious, life-threatening, and/or fatal respiratory depression has occurred in patients treated with SUBSYS, including following use in opioid non-tolerant patients and improper dosing. Monitor for respiratory depression, especially during initiation of SUBSYS or following a dose increase. The substitution of SUBSYS for any other fentanyl product may result in fatal overdose [see Warnings and Precautions (5.1)]

Due to the risk of respiratory depression, SUBSYS is contraindicated in the management of acute or postoperative pain including headache/migraine and in opioid non-tolerant patients. [see Contraindications (4)]

Accidental INGESTION
Accidental ingestion of even one dose of SUBSYS especially by children, can result in a fatal overdose of fentanyl [see Warnings and Precautions (5.2)] .

Death has been reported in children who have accidentally ingested transmucosal immediate-release fentanyl products. SUBSYS must be kept out of reach of children [see Warnings and Precautions (5.2); How Supplied/Storage and Handling (16)].

Cytochrome P450 3A4 Interaction
The concomitant use of SUBSYS with all cytochrome P450 3A4 inhibitors may result in an increase in fentanyl plasma concentrations, which could increase or prolong adverse reactions and may cause potentially fatal respiratory depression. In addition, discontinuation of a concomitantly used cytochrome P450 3A4 inducer may result in an increase in fentanyl plasma concentration. Monitor patients receiving SUBSYS and any CYP3A4 inhibitor or inducer [see Warnings and Precautions (5.3), Drug Interactions (7), Clinical Pharmacology (12.3)] .

Risks From Concomitant Use With Benzodiazepines Or Other CNS Depressants
Concomitant use of opioids with benzodiazepines or other central nervous system (CNS) depressants, including alcohol, may result in profound sedation, respiratory depression, coma, and death [see Warnings and Precautions (5.4), Drug Interactions (7)].

- Reserve concomitant prescribing of SUBSYS and benzodiazepines or other CNS depressants for use in patients for whom alternative treatment options are inadequate.
- Limit dosages and durations to the minimum required.
- Follow patients for signs and symptoms of respiratory depression and sedation.

Risk of Medication Errors
Substantial differences exist in the pharmacokinetic profile of SUBSYS compared to other fentanyl products that result in clinically important differences in the extent of absorption of fentanyl that could result in fatal overdose [see Dosage and Administration (2.1), Warnings and Precautions (5.5)] .

- When prescribing, do not convert patients on a mcg per mcg basis from any other fentanyl products to SUBSYS.
- When dispensing, do not substitute a SUBSYS prescription for other fentanyl products.

Addiction, Abuse, and Misuse
SUBSYS exposes patients and other users to the risks of opioid addiction, abuse, and misuse, which can lead to overdose and death. Assess each patient’s risk prior to prescribing SUBSYS, and monitor all patients regularly for the development of these behaviors and conditions [see Warnings and Precautions (5.6)] .

Risk Evaluation and Mitigation Strategy (REMS) Access Program
Because of the risk for misuse, abuse, addiction, and overdose, SUBSYS is available only through a restricted program required by the Food and Drug Administration, called a Risk Evaluation and Mitigation Strategy (REMS). Under the Transmucosal Immediate Release Fentanyl (TIRF) REMS, pharmacies, outpatients, and healthcare professionals who prescribe to outpatients must enroll in the program. [see Warnings and Precautions (5.7)]. Further information is available at www.TIRFREMSaccess.com or by calling 1-866-822-1483.

Neonatal Opioid Withdrawal Syndrome
Prolonged use of SUBSYS during pregnancy can result in neonatal opioid withdrawal syndrome, which may be life-threatening if not recognized and treated, and requires management according to protocols developed by neonatology experts. If opioid use is required for a prolonged period in a pregnant woman, advise the patient of the risk of neonatal opioid withdrawal syndrome and ensure that appropriate treatment will be available [ see Warnings and Precautions (5.8) ].

1 INDICATIONS AND USAGE

SUBSYS is indicated for the management of breakthrough pain in cancer patients 18 years of age and older who are already receiving and who are tolerant to around-the-clock opioid therapy for their underlying persistent cancer pain.

Patients considered opioid tolerant are those who are taking for one week or longer, around-the-clock medicine consisting of at least 60 mg of oral morphine per day, at least 25 mcg of transdermal fentanyl per hour, at least 30 mg of oral oxycodone per day, at least 8 mg of oral hydromorphone per day, or at least 25 mg oral oxymorphone per day, or at least 60mg oral hydrocodone per day, or an equianalgesic dose of another opioid daily for a week or longer. Patients must remain on around-the-clock opioids when taking SUBSYS.

Limitations of Use:

- Not for use in opioid non-tolerant patients.
- Not for use in the management of acute or postoperative pain, including headache/migraine, dental pain, or in the emergency room [see Contraindications (4)].
- As part of the Transmucosal Immediate-Release Fentanyl (TIRF) REMS ACCESS Program, SUBSYS may be dispensed only to outpatients enrolled in the program. [see Warnings and Precautions (5.7)] . For inpatient administration of SUBSYS, patient enrollment is not required.

2 DOSAGE AND ADMINISTRATION

2.1 Important Dosage and Administration Instructions

- Healthcare professionals who prescribe SUBSYS on an outpatient basis must enroll in the TIRF REMS ACCESS program and comply with the requirements of the REMS to ensure safe use of SUBSYS. [see Warnings and Precautions (5.7)]
- Use the lowest effective dosage for the shortest duration consistent with individual patient treatment goals [see Warnings and Precautions (5)].
- It is important to minimize the number of strengths available to patients at any time to prevent confusion and possible overdose.
- Initiate the dosing regimen for each patient individually, taking into account the patient's severity of pain, patient response, prior analgesic treatment experience, and risk factors for addiction, abuse, and misuse [see Warnings and Precautions (5.6)] .
- Monitor patients closely for respiratory depression, especially within the first 24-72 hours of initiating therapy and following dosage increases with SUBSYS and adjust the dosage accordingly [see Warnings and Precautions (5.1)].
- Instruct patients and caregivers to take steps to store SUBSYS securely and to properly dispose of unused SUBSYS as soon as no longer needed [see Warnings and Precautions (5.2, 5.6), Patient Counseling Information (17)].
- Other TIRF formulations and SUBSYS are not equivalent. DO NOT substitute a SUBSYS prescription for any other TIRF formulation under any circumstances. Do not convert patients on a mcg per mcg basis from any other fentanyl product to SUBSYS [see Warnings and Precautions (5.5)]
- SUBSYS is not bioequivalent with other fentanyl products. Do not convert patients on a mcg per mcg basis from other fentanyl products. There are no conversion directions available for patients on any other fentanyl products, other than Actiq. (Note: This includes oral, transdermal, or parenteral formulations of fentanyl.) [see Warnings and Precautions (5.5)].
- SUBSYS is NOT a generic version of any other oral transmucosal fentanyl product [see Warnings and Precautions (5.5)] .

2.2 Patient Access to Naloxone for the Emergency Treatment of Opioid Overdose

Discuss the availability of naloxone for the emergency treatment of opioid overdose with the patient and caregiver and assess the potential need for access to naloxone, both when initiating and renewing treatment with SUBSYS [see Warnings and Precautions (5.1), Patient Counseling Information (17)] .

Inform patients and caregivers about the various ways to obtain naloxone as permitted by individual state naloxone dispensing and prescribing requirements or guidelines (e.g., by prescription, directly from a pharmacist, or as part of a community-based program).

Consider prescribing naloxone, based on the patient’s risk factors for overdose, such as concomitant use of CNS depressants, a history of opioid use disorder, or prior opioid overdose. The presence of risk factors for overdose should not prevent the proper management of pain in any given patient [see Warnings and Precautions (5.1, 5.4, 5.6)] .

Consider prescribing naloxone if the patient has household members (including children) or other close contacts at risk for accidental ingestion or overdose.

2.3 Initial Dosage

Initiate treatment with SUBSYS for all patients (including those switching from another fentanyl product) using ONE 100 mcg spray sublingually.

Prescribe an initial titration supply of 100 mcg SUBSYS units, which limits the number of units in the home during titration.

Avoid prescribing a higher dose until patients have used up all units to prevent confusion and possible overdose.

Conversion from Actiq to SUBSYS

The initial dose of SUBSYS is always 100 mcg with the only exception of patients already using Actiq.

1. For patients being converted from Actiq, prescribers must use the Initial Dosing Recommendations for Patients on Actiq table below (Table 1). Patients must be instructed to stop the use of Actiq and dispose of any remaining units.
  Table 1. Initial Dosing Recommendations for Patients on ACTIQ
  Current ACTIQ Dose (mcg) | Initial SUBSYS Dose (mcg)
  200 | 100 mcg spray
  400 | 100 mcg spray
  600 | 200 mcg spray
  800 | 200 mcg spray
  1200 | 400 mcg spray
  1600 | 400 mcg spray
2. For patients converting from Actiq doses 400 mcg and below, titration should be initiated with 100 mcg SUBSYS and should proceed using multiples of this strength.
3. For patients converting from Actiq doses of 600 and 800 mcg, titration should be initiated with 200 mcg SUBSYS and should proceed using multiples of this strength.
4. For patients converting from Actiq doses of 1200 and 1600 mcg, titration should be initiated with 400 mcg SUBSYS and should proceed using multiples of this strength.

2.4 Dosage Modifications in Patients with Oral Mucositis

In cancer patients with mucositis, exposure to SUBSYS was greater than in patients without mucositis. For patients with Grade 1 mucositis, the increased maximum serum concentration and overall exposure requires closer monitoring for respiratory depression and central nervous system depression, particularly during initiation of therapy with SUBSYS. For patients with Grade 2 mucositis or higher, avoid use of SUBSYS unless the benefits outweigh the potential risk of respiratory depression from increased exposure. [see Clinical Pharmacology (12.3)]

2.5 Titration and Maintenance of Therapy

Individually titrate SUBSYS to a dose that provides adequate analgesia and minimizes adverse reactions.

1. From the 100 mcg initial dose, closely follow patients and change the dosage level until the patient reaches a dose that provides adequate analgesia using a single SUBSYS dose per breakthrough cancer pain episode with tolerable side effects. Patients should record their use of SUBSYS over several episodes of breakthrough cancer pain and review their experience with their physicians to determine if a dosage adjustment is warranted.
2. For each breakthrough pain episode treated, if pain is not relieved after 30 minutes, patients may take ONLY ONE additional dose of the same strength for that episode. Thus patients should take a maximum of two doses of SUBSYS for any breakthrough pain episode.
3. Patients MUST wait at least 4 hours before treating another episode of breakthrough pain with SUBSYS.
4. If there is a need to titrate to a 200 mcg dose, prescribe 200 mcg SUBSYS units.
5. Subsequent titration steps are 400 mcg, 600 mcg, 800 mcg, 1200 mcg and 1600 mcg. See Table 2.
6. To reduce the risk of overdose during titration, patients should have only one strength of SUBSYS available at any time.

Table 2. Titration Steps
SUBSYS DOSE | Using
100 mcg | 1 × 100 mcg unit
200 mcg | 1 × 200 mcg unit
400 mcg | 1 × 400 mcg unit
600 mcg | 1 × 600 mcg unit
800 mcg | 1 × 800 mcg unit
1200 mcg | 2 × 600 mcg unit
1600 mcg | 2 × 800 mcg unit

SUBSYS Titration Process

Once titrated to a dose that provides adequate pain relief and tolerable side effects, patients should generally use ONLY ONE SUBSYS dose of the appropriate strength per breakthrough pain episode.

On those occasions when the breakthrough pain episode is not relieved within 30 minutes after administration of the SUBSYS dose, the patient may take ONLY ONE additional dose using the same strength for that episode.

Patients MUST wait at least 4 hours before treating another episode of breakthrough pain with SUBSYS. Once a successful dose has been found, patients should limit consumption to four or fewer doses per day.

Dosage adjustment of SUBSYS may be required in some patients in order to continue to provide adequate relief of breakthrough pain.

If signs of excessive opioid effects appear following administration of a single SUBSYS dose, subsequent doses should be decreased.

Generally, only increase the SUBSYS dose when a single administration of the current dose fails to adequately treat the breakthrough pain episode for several consecutive episodes.

If the patient experiences greater than four breakthrough pain episodes per day, the dose of the maintenance (around-the-clock) opioid used for persistent pain should be re-evaluated. In addition, if pain worsens, re-evaluate the patient for changes in the underlying pain condition.

2.6 Discontinuation of SUBSYS

For patients no longer requiring opioid therapy, consider discontinuing SUBSYS along with a gradual downward titration of other opioids to minimize possible withdrawal effects. In patients who continue to take their chronic opioid therapy for persistent pain but no longer require treatment for breakthrough pain, SUBSYS therapy can usually be discontinued immediately. [ see Drug Abuse and Dependence (9.3) ].

2.7 Disposal of SUBSYS

Patients and caregivers must be advised to dispose of used unit dose systems immediately after use and any unneeded unit dose systems remaining from a prescription as soon as they are no longer needed. Consumed units represent a special risk because they are no longer protected by the child resistant blister package, yet may contain enough medicine to be fatal to a child. [see Patient Counseling Information (17)].

Charcoal-lined disposal pouches are provided with every carton dispensed. A charcoal-lined disposal pouch is to be used by patients or their caregivers to dispose of the contents of any unneeded unit dose systems when they are no longer needed. Instructions for usage of the charcoal-lined disposal pouch are included in the Medication Guide and Instructions for Use.

3 DOSAGE FORMS AND STRENGTHS

SUBSYS is a sublingual spray available in 100 mcg, 200 mcg, 400 mcg, 600 mcg, 800 mcg, 1200 mcg, and 1600 mcg strengths. SUBSYS is supplied as spray units consisting of a white actuator attached to a light purple vial holder [see How Supplied/Storage and Handling (16)] . 100 mcg, 200 mcg, 400 mcg, 600 mcg, and 800 mcg doses are delivered as a single unit (spray). To administer 1200 mcg and 1600 mcg doses, two units (sprays) must be used.

Each dosage strength is differentiated by the color of the blister package, and carton as described below in Table 3. The strength of the spray unit is indicated on the actuator.

Table 3. Subsys Strengths
Dosage Strength (fentanyl base) | Using | Carton/Blister Package Color
100 mcg | 1 × 100 mcg unit packaged in a single blister | Blue
200 mcg | 1 × 200 mcg unit packaged in a single blister | Green
400 mcg | 1 × 400 mcg unit packaged in a single blister | Magenta (Pink)
600 mcg | 1 × 600 mcg unit packaged in a single blister | Purple
800 mcg | 1 × 800 mcg unit packaged in a single blister | Orange
1200 mcg | 2 × 600 mcg units packaged in a single blister | Brown
1600 mcg | 2 × 800 mcg units packaged in a single blister | Red

4 CONTRAINDICATIONS

SUBSYS is contraindicated in:

- Opioid non-tolerant patients: Life-threatening respiratory depression and death could occur at any dose in opioid non-tolerant patients [see Indications and Usage (1); Warnings and Precautions (5.1)] .
- Acute or postoperative pain including headache/migraine and dental pain, or in the emergency department [see Indications and Usage (1)] .
- Acute or severe bronchial asthma in an unmonitored setting or in the absence of resuscitative equipment [see Warnings and Precautions (5.9)].
- Known or suspected gastrointestinal obstruction, including paralytic ileus [see Warnings and Precautions (5.14)].
- Known hypersensitivity (e.g., anaphylaxis) to fentanyl or components of SUBSYS [see Adverse Reactions (6.2)] .

5 WARNINGS AND PRECAUTIONS

5.1 Life-Threatening Respiratory Depression

Serious, life-threatening, or fatal respiratory depression has been reported with the use of opioids, even when used as recommended. Respiratory depression, if not immediately recognized and treated, may lead to respiratory arrest and death. Management of respiratory depression may include close observation, supportive measures, and use of opioid antagonists, depending on the patient’s clinical status [see Overdosage (10)] . Carbon dioxide (CO2) retention from opioid-induced respiratory depression can exacerbate the sedating effects of opioids.

While serious, life-threatening, or fatal respiratory depression can occur at any time during the use of SUBSYS, the risk is greatest during the initiation of therapy or following a dosage increase. Monitor patients closely for respiratory depression, especially within the first 24-72 hours of initiating therapy with and following dosage increases of SUBSYS.

To reduce the risk of respiratory depression, proper dosing and titration of SUBSYS are essential [see Dosage and Administration (2.5)] . Overestimating the SUBSYS dosage can result in a fatal overdose with the first dose. The substitution of SUBSYS for any other fentanyl product may result in fatal overdose [see Warnings and Precautions (5.5)].

SUBSYS could be fatal to individuals for whom it is not prescribed and for those who are not opioid-tolerant.

Accidental ingestion or exposure to even one dose of SUBSYS, especially in children, can result in respiratory depression and death due to an overdose of fentanyl.

Educate patients and caregivers on how to recognize respiratory depression and emphasize the importance of calling 911 or getting emergency medical help right away in the event of a known or suspected overdose [see Patient Counseling Information (17)].

Opioids can cause sleep-related breathing disorders including central sleep apnea (CSA) and sleep-related hypoxemia. Opioid use increases the risk of CSA in a dose-dependent fashion. In patients who present with CSA, consider decreasing the opioid dosage using best practices for opioid taper [see Dosage and Administration (2.5)].

Patient Access to Naloxone for the Emergency Treatment of Opioid Overdose

Discuss the availability of naloxone for the emergency treatment of opioid overdose with the patient and caregiver and assess the potential need for access to naloxone, both when initiating and renewing treatment with SUBSYS. Inform patients and caregivers about the various ways to obtain naloxone as permitted by individual state naloxone dispensing and prescribing requirements or guidelines (e.g., by prescription, directly from a pharmacist, or as part of a community-based program). Educate patients and caregivers on how to recognize respiratory depression and emphasize the importance of calling 911 or getting emergency medical help, even if naloxone is administered [see Patient Counseling Information (17)].

Consider prescribing naloxone, based on the patient’s risk factors for overdose, such as concomitant use of CNS depressants, a history of opioid use disorder, or prior opioid overdose. The presence of risk factors for overdose should not prevent the proper management of pain in any given patient. Also consider prescribing naloxone if the patient has household members (including children) or other close contacts at risk for accidental ingestion or overdose. If naloxone is prescribed, educate patients and caregivers on how to treat with naloxone. [see Warnings and Precautions (5.4, 5.6), Patient Counseling Information (17)].

5.2 Increased Risk of Overdose in Children Due to Accidental Ingestion

Death has been reported in children who have accidentally ingested transmucosal immediate–release fentanyl products.

Patients and their caregivers must be informed that SUBSYS contains a medicine in an amount which can be fatal to a child. Physicians and dispensing pharmacists must specifically question patients or caregivers about the presence of children in the home (on a full time or visiting basis) and counsel them regarding the dangers to children from inadvertent exposure.

Patients and their caregivers must be instructed to keep both used and unused dosage units out of the reach of children. While all units should be disposed of immediately after use, partially consumed units represent a special risk to children. In the event that a unit is not completely consumed it must be properly disposed as soon as possible [ see Patient Counseling Information (17) ].

Detailed instructions for the proper storage, administration, disposal, and important instructions for managing an overdose of SUBSYS are provided in the SUBSYS Medication Guide. Encourage patients to read this information in its entirety and give them an opportunity to have their questions answered.

5.3 Risks of Concomitant Use or Discontinuation of Cytochrome P450 3A4 Inhibitors and Inducers

Concomitant use of SUBSYS with a CYP3A4 inhibitor, such as macrolide antibiotics (e.g., erythromycin), azole-antifungal agents (e.g., ketoconazole), and protease inhibitors (e.g., ritonavir), may increase plasma concentrations of fentanyl and prolong opioid adverse reactions, which may cause potentially fatal respiratory depression [ see Warnings and Precautions (5.9) ], particularly when an inhibitor is added after a stable dose of SUBSYS is achieved. Similarly, discontinuation of a CYP3A4 inducer, such as rifampin, carbamazepine, and phenytoin, in SUBSYS-treated patients may increase fentanyl plasma concentrations and prolong opioid adverse reactions. When using SUBSYS with CYP3A4 inhibitors or discontinuing CYP3A4 inducers in SUBSYS-treated patients, monitor patients closely at frequent intervals and consider dosage reduction of SUBSYS until stable drug effects are achieved [see Drug Interactions (7)] .

Concomitant use of SUBSYS with CYP3A4 inducers or discontinuation of an CYP3A4 inhibitor could decrease fentanyl plasma concentrations, decrease opioid efficacy or, possibly, lead to a withdrawal syndrome in a patient who had developed physical dependence to fentanyl. When using SUBSYS with CYP3A4 inducers or discontinuing CYP3A4 inhibitors, monitor patients closely at frequent intervals and consider increasing the opioid dosage if needed to maintain adequate analgesia or if symptoms of opioid withdrawal occur [ see Drug Interactions (7)] .

5.4 Risks from Concomitant Use with Benzodiazepines or Other CNS Depressants

Profound sedation, respiratory depression, coma, and death may result from the concomitant use of SUBSYS with benzodiazepines or other CNS depressants (e.g., non-benzodiazepine sedatives/hypnotics, anxiolytics, tranquilizers, muscle relaxants, general anesthetics, antipsychotics, other opioids, alcohol). Because of these risks, reserve concomitant prescribing of these drugs for use in patients for whom alternative treatment options are inadequate.

Observational studies have demonstrated that concomitant use of opioid analgesics and benzodiazepines increases the risk of drug-related mortality compared to use of opioid analgesics alone. Because of similar pharmacological properties, it is reasonable to expect similar risk with the concomitant use of other CNS depressant drugs with opioid analgesics [see Drug Interactions (7)] .

If the decision is made to prescribe a benzodiazepine or other CNS depressant concomitantly with an opioid analgesic, prescribe the lowest effective dosages and minimum durations of concomitant use. In patients already receiving an opioid analgesic, prescribe a lower initial dose of the benzodiazepine or other CNS depressant than indicated in the absence of an opioid, and titrate based on clinical response. If an opioid analgesic is initiated in a patient already taking a benzodiazepine or other CNS depressant, prescribe a lower initial dose of the opioid analgesic, and titrate based on clinical response. Follow patients closely for signs and symptoms of respiratory depression and sedation.

If concomitant use is warranted, consider prescribing naloxone for the emergency treatment of opioid overdose [see Dosage and Administration (2.2), Warnings and Precautions (5.1)].

Advise both patients and caregivers about the risks of respiratory depression and sedation when SUBSYS is used with benzodiazepines or other CNS depressants (including alcohol and illicit drugs). Advise patients not to drive or operate heavy machinery until the effects of concomitant use of the benzodiazepine or other CNS depressant have been determined. Screen patients for risk of substance use disorders, including opioid abuse and misuse, and warn them of the risk for overdose and death associated with the use of additional CNS depressants including alcohol and illicit drugs [see Drug Interactions (7) and Patient Counseling Information (17)].

5.5 Risk of Medication Errors

When prescribing, DO NOT convert a patient to SUBSYS from any other fentanyl product on a mcg per mcg basis as SUBSYS and other fentanyl products are not equivalent on a microgram per microgram basis.

SUBSYS is NOT a generic version of other transmucosal immediate release fentanyl (TIRF) formulations. When dispensing, DO NOT substitute a SUBSYS prescription for any other TIRF formulation under any circumstances. Other TIRF formulations and SUBSYS are not equivalent. Substantial differences exist in the pharmacokinetic profile of SUBSYS compared to other fentanyl products including other TIRF formulations that result in clinically important differences in the rate and extent of absorption of fentanyl. As a result of these differences, the substitution of SUBSYS for any other fentanyl product may result in a fatal overdose.

There are no safe conversion directions available for patients on any other fentanyl products (Note: This includes oral, transdermal, or parenteral formulations of fentanyl.) [see Dosage and Administration (2.1)] . Therefore, for opioid tolerant patients, the initial dose of SUBSYS should always be ONE 100 mcg spray. Individually titrate each patient’s dose to provide adequate analgesia while minimizing side effects [see Dosage and Administration (2.4)] .

5.6 Addiction, Abuse, and Misuse

SUBSYS contains fentanyl, a Schedule II controlled substance. As an opioid, SUBSYS exposes users to the risks of addiction, abuse, and misuse [see Drug Abuse and Dependence (9)].

Although the risk of addiction in any individual is unknown, it can occur in patients appropriately prescribed SUBSYS. Addiction can occur at recommended dosages and if the drug is misused or abused.

Assess each patient’s risk for opioid addiction, abuse, or misuse prior to prescribing SUBSYS, and monitor all patients receiving SUBSYS for the development of these behaviors or conditions. Risks are increased in patients with a personal or family history of substance abuse (including drug or alcohol abuse or addiction) or mental illness (e.g., major depression). The potential for these risks should not, however, prevent the proper management of pain in any given patient. Patients at increased risk may be prescribed opioids such as SUBSYS, but use in such patients necessitates intensive counseling about the risks and proper use of SUBSYS along with intensive monitoring for signs of addiction, abuse, and misuse. Consider prescribing naloxone for the emergency treatment of opioid overdose [see Dosage and Administration (2.2), Warnings and Precautions (5.1)].

Opioids are sought by drug abusers and people with addiction disorders and are subject to criminal diversion. Consider these risks when prescribing or dispensing SUBSYS. Strategies to reduce these risks include prescribing the drug in the smallest appropriate quantity and advising the patient on the proper disposal of unused drug [see Patient Counseling Information (17)]. Contact local state professional licensing board or state controlled substances authority for information on how to prevent and detect abuse or diversion of this product.

5.7 Transmucosal Immediate Release Fentanyl (TIRF) Risk Evaluation and Mitigation Strategy (REMS) Access Program

Because of the risk of accidental exposure, misuse, abuse, addiction, and overdose [see Warnings and Precautions (5.1)], SUBSYS is available only through a restricted program under a REMS called the TIRF REMS. Under the TIRF REMS, healthcare professionals who prescribe to outpatients, the outpatients themselves, and pharmacies, are required to enroll in the program.

Notable requirements of the TIRF REMS are:

- Prescribers for outpatient use must be certified with the REMS program by enrolling and completing training. Prescribers must document opioid tolerance with every SUBSYS prescription.
- Outpatients must be enrolled in the REMS program and must be opioid tolerant to receive SUBSYS [see Dosage and Administration (2.1)] .
- Outpatient pharmacies must be certified with the REMS program and verify documentation of opioid tolerance with every SUBSYS prescription.
- Inpatient pharmacies must be certified with the REMS program and develop policies and procedures to verify opioid tolerance in inpatients who require SUBSYS while hospitalized.
- Wholesalers and distributers must enroll in the REMS program and distribute only to certified pharmacies.
- Further information, including a list of certified pharmacies and enrolled distributors, is available at www.tirfremsaccess.com or by calling 1-866-822-1483.

5.8 Neonatal Opioid Withdrawal Syndrome

Prolonged use of SUBSYS during pregnancy can result in withdrawal in the neonate. Neonatal opioid withdrawal syndrome, unlike opioid withdrawal syndrome in adults, may be life-threatening if not recognized and treated, and requires management according to protocols developed by neonatology experts. Observe newborns for signs of neonatal opioid withdrawal syndrome and manage accordingly. Advise pregnant women using opioids for a prolonged period of the risk of neonatal opioid withdrawal syndrome and ensure that appropriate treatment will be available [see Use in Specific Populations (8.1), Patient Counseling Information (17)].

5.9 Life-Threatening Respiratory Depression in Patients with Chronic Pulmonary Disease or in Elderly, Cachectic, or Debilitated Patients

The use of SUBSYS in patients with acute or severe bronchial asthma in an unmonitored setting or in the absence of resuscitative equipment is contraindicated.

Patients with Chronic Pulmonary Disease: SUBSYS treated patients with significant chronic obstructive pulmonary disease or cor pulmonale, and those with a substantially decreased respiratory reserve, hypoxia, hypercapnia, or pre-existing respiratory depression are at increased risk of decreased respiratory drive including apnea, even at recommended dosages of SUBSYS [see Warnings and Precautions (5.1)] .

Elderly, Cachectic, or Debilitated Patients: Life-threatening respiratory depression is more likely to occur in elderly, cachectic, or debilitated patients because they may have altered pharmacokinetics or altered clearance compared to younger, healthier patients [see Warnings and Precautions (5.1)] .

Monitor such patients closely, particularly when initiating and titrating SUBSYS and when SUBSYS is given concomitantly with other drugs that depress respiration [see Warnings and Precautions (5.9)] . Alternatively, consider the use of non-opioid analgesics in these patients.

5.10 Serotonin Syndrome with Concomitant Use of Serotonergic Drugs

Cases of serotonin syndrome, a potentially life-threatening condition, have been reported during concomitant use of SUBSYS with serotonergic drugs. Serotonergic drugs include selective serotonin reuptake inhibitors (SSRIs), serotonin and norepinephrine reuptake inhibitors (SNRIs), tricyclic antidepressants (TCAs), triptans, 5-HT3 receptor antagonists, drugs that affect the serotonergic neurotransmitter system (e.g., mirtazapine, trazodone, tramadol), certain muscle relaxants (i.e., cyclobenzaprine, metaxalone), and drugs that impair metabolism of serotonin (including MAO inhibitors, both those intended to treat psychiatric disorders and also others, such as linezolid and intravenous methylene blue) [see Drug Interactions (7)] . This may occur within the recommended dosage range.

Serotonin syndrome symptoms may include mental status changes (e.g., agitation, hallucinations, coma), autonomic instability (e.g., tachycardia, labile blood pressure, hyperthermia), neuromuscular aberrations (e.g., hyperreflexia, incoordination, rigidity), and/or gastrointestinal symptoms (e.g., nausea, vomiting, diarrhea). The onset of symptoms generally occurs within several hours to a few days of concomitant use, but may occur later than that. Discontinue SUBSYS if serotonin syndrome is suspected.

5.11 Adrenal Insufficiency

Cases of adrenal insufficiency have been reported with opioid use, more often following greater than one month of use. Presentation of adrenal insufficiency may include non-specific symptoms and signs including nausea, vomiting, anorexia, fatigue, weakness, dizziness, and low blood pressure. If adrenal insufficiency is suspected, confirm the diagnosis with diagnostic testing as soon as possible. If adrenal insufficiency is diagnosed, treat with physiologic replacement doses of corticosteroids. Wean the patient off of the opioid to allow adrenal function to recover and continue corticosteroid treatment until adrenal function recovers. Other opioids may be tried as some cases reported use of a different opioid without recurrence of adrenal insufficiency. The information available does not identify any particular opioids as being more likely to be associated with adrenal insufficiency.

5.12 Severe Hypotension

SUBSYS may cause severe hypotension including orthostatic hypotension and syncope in ambulatory patients. There is increased risk in patients whose ability to maintain blood pressure has already been compromised by a reduced blood volume or concurrent administration of certain CNS depressant drugs (e.g. phenothiazines or general anesthetics) [see Drug Interactions (7)] . Monitor these patients for signs of hypotension after initiating or titrating the dosage of SUBSYS. In patients with circulatory shock, SUBSYS may cause vasodilation that can further reduce cardiac output and blood pressure. Avoid the use of SUBSYS in patients with circulatory shock.

5.13 Risks of Use in Patients with Increased Intracranial Pressure, Brain Tumors, Head Injury, or Impaired Consciousness

In patients who may be susceptible to the intracranial effects of CO2 retention (e.g., those with evidence of increased intracranial pressure or brain tumors), SUBSYS may reduce respiratory drive, and the resultant CO2 retention can further increase intracranial pressure. Monitor such patients for signs of sedation and respiratory depression, particularly when initiating therapy with SUBSYS.

Opioids may also obscure the clinical course in a patient with a head injury. Avoid the use of SUBSYS in patients with impaired consciousness or coma.

5.14 Risks of Use in Patients with Gastrointestinal Conditions

SUBSYS is contraindicated in patients with known or suspected gastrointestinal obstruction, including paralytic ileus.

The fentanyl in SUBSYS may cause spasm of the sphincter of Oddi. Opioids may cause increases in serum amylase. Monitor patients with biliary tract disease, including acute pancreatitis for worsening symptoms.

5.15 Increased Risk of Seizures in Patients with Seizure Disorders

The fentanyl in SUBSYS may increase the frequency of seizures in patients with seizure disorders, and may increase the risk of seizures occurring in other clinical settings associated with seizures. Monitor patients with a history of seizure disorders for worsened seizure control during SUBSYS therapy.

5.16 Risks of Driving and Operating Machinery

SUBSYS may impair the mental or physical abilities needed to perform potentially hazardous activities such as driving a car or operating machinery. Warn patients not to drive or operate dangerous machinery unless they are tolerant to the effects of SUBSYS and know how they will react to the medication.

5.17 Cardiac Disease

Intravenous fentanyl may produce bradycardia. Therefore, use SUBSYS with caution in patients with bradyarrhythmias.

6 ADVERSE REACTIONS

The following serious adverse reactions are described, or described in greater detail, in other sections:

- Life-Threatening Respiratory Depression [see Warnings and Precautions (5.1)]
- Interactions with Benzodiazepines and other CNS Depressants [see Warnings and Precautions (5.4)
- Addiction, Abuse, and Misuse [see Warnings and Precautions (5.6)]
- Neonatal Opioid Withdrawal Syndrome [see Warnings and Precautions (5.8)]
- Serotonin Syndrome [see Warnings and Precautions (5.10)]
- Adrenal Insufficiency [see Warnings and Precautions (5.11)]
- Severe Hypotension [see Warnings and Precautions (5.12)]
- Gastrointestinal Adverse Reactions [see Warnings and Precautions (5.14)]
- Seizures [see Warnings and Precautions (5.15)]

6.1 Clinical Trials Experience

Because clinical trials are conducted under widely varying conditions, adverse reaction rates observed in the clinical trials of a drug cannot be directly compared to rates in the clinical trials of another drug and may not reflect the rates observed in practice.

The safety of SUBSYS has been evaluated in a total of 359 opioid-tolerant patients with breakthrough cancer pain. The duration of SUBSYS use varied during the open-label study. Safety data from a long-term extension study showed that the average duration of therapy in the open-label study was 66 days. The maximum duration of therapy was 149 days. The dose range studied in these trials ranged from 100 mcg per dose to 1600 mcg per dose.

The most serious adverse reactions associated with all opioids including SUBSYS are respiratory depression (potentially leading to apnea or respiratory arrest), circulatory depression, hypotension, and shock. Follow all patients for symptoms of respiratory depression.

The most common adverse reaction leading to discontinuation of SUBSYS was nausea. There were also adverse reactions of abdominal distension, anorexia, confusional state, disorientation, somnolence, and constipation.

The clinical trials of SUBSYS were designed to evaluate safety and efficacy in treating breakthrough cancer pain; all patients were also taking concomitant opioids, such as sustained-release morphine or transdermal fentanyl, for their persistent cancer pain. The adverse event data presented here reflect the actual percentage of patients experiencing each adverse effect among patients who received SUBSYS for breakthrough cancer pain along with a concomitant opioid for persistent cancer pain.

Table 4 lists adverse reactions with an overall frequency of 5% or greater that occurred during titration in the clinical trials. Adverse reactions are listed in descending order of frequency within each system organ class.

Table 4. Percent of Patients with Specific Adverse Events During Titration in the Clinical Trials (Events in 5% or More of Patients)
System Organ Class | Titration n=359 (%)
Gastrointestinal Disorders
Nausea | 47 (13.1%)
Vomiting | 37 (10.3%)
Constipation | 18 (5.0%)
Nervous System Disorders
Somnolence | 34 (9.5%)
Dizziness | 26 (7.2%)
A patient was counted only once within each category.

The following adverse reactions occurred during titration in the clinical trials with an overall frequency of 1% or greater and are listed in descending order of frequency within each system organ class.

Cardiac Disorders: Tachycardia

Gastrointestinal Disorders: Diarrhea, stomatitis, dry mouth

General Disorders and Administration Site Conditions: Application site irritation, pyrexia, edema peripheral, fatigue, asthenia

Metabolism and Nutrition Disorders: Decreased appetite

Nervous System Disorders: Lethargy, sedation, tremor, headache

Psychiatric Disorders: Depression, confusional state, hallucination, insomnia

Respiratory, Thoracic and Mediastinal Disorders: Dyspnea

Skin and Subcutaneous Tissue Disorders: Pruritus

The following reactions occurred during titration in the clinical trials with an overall frequency of less than 1% and are listed in descending order of frequency within each system organ class.

Eye Disorders: Vision blurred, dry eye

Gastrointestinal Disorders: Abdominal pain

Infections and Infestations: Oral candidiasis, cellulitis

Injury, Poisoning and Procedural Complications: Fall

Metabolism and Nutrition Disorders: Dehydration, anorexia

Musculoskeletal and Connective Tissue Disorders: Back pain, arthralgia, joint swelling

Psychiatric Disorders: Anxiety, agitation

Renal and Urinary Disorders: Urinary retention

Respiratory, Thoracic and Mediastinal Disorders: Cough, increased bronchial secretion, dysphonia, pharyngolaryngeal pain

Skin and Subcutaneous Tissue Disorders: Hyperhidrosis

Vascular Disorders: Hot flush

Table 5 lists adverse reactions with an overall frequency of 5% or greater for the total safety database subsequent to titration during the clinical trials.

Table 5. Adverse Reactions Subsequent to Titration in 5% or More of Patients
System Organ Class | Dosing n=269
Gastrointestinal Disorders
Vomiting | 43 (16.0%)
Nausea | 28 (10.4%)
Constipation | 28 (10.4%)
General Disorders and Administration Site Conditions
Asthenia | 26 (9.7%)
Respiratory, Thoracic and Mediastinal Disorders
Dyspnea | 28 (10.4%)
Psychiatric Disorders
Anxiety | 16 (5.9%)
A patient was counted only once within each category.

The following adverse reactions occurred during the dosing period of the clinical trial with an overall frequency of 1% or greater and are listed in descending order of frequency within each system organ class.

Blood and Lymphatic System Disorders: Anemia, neutropenia, lymphadenopathy, thrombocytopenia, leukopenia

Cardiac Disorders: Tachycardia, sinus tachycardia

Gastrointestinal Disorders: Diarrhea, stomatitis, abdominal pain, abdominal distension, gastritis, dysphagia, dyspepsia, gastroesophageal reflux disease, ascites, hematemesis

General Disorders and Administration Site Conditions: Edema peripheral, fatigue, pyrexia, chest pain, drug withdrawal syndrome, chills, irritability, malaise, application site irritation

Infections and Infestations: Oral candidiasis, pneumonia, urinary tract infection, oral herpes, gastroenteritis, laryngitis

Injury, Poisoning and Procedural Complications: Contusion

Investigations: Weight decreased, aspartate aminotransferase increased, blood alkaline phosphatase increased, blood glucose increased, blood lactate increased

Metabolism and Nutrition Disorders: Anorexia, dehydration, hypokalemia, decreased appetite, hyponatremia, hypocalcemia, hypoalbuminemia, cachexia

Musculoskeletal and Connective Tissue Disorders: Back pain, arthralgia, muscular weakness

Nervous System Disorders: Hypoesthesia, lethargy, sedation, tremor, somnolence, headache, dizziness

Psychiatric Disorders: Depression, restlessness, agitation, confusional state, insomnia, hallucination, disorientation

Renal and Urinary Disorders: hypertension, hypotension

Respiratory, Thoracic and Mediastinal Disorders: Cough, increased bronchial secretion, wheezing, pharyngolaryngeal pain, hypoxia, dyspnea exertional

Skin and Subcutaneous Tissue Disorders: hyperhidrosis, pruritus

In a single-dose mucositis study, a group of patients with Grade 1 or 2 oral mucositis (n=9) and without oral mucositis (n=9) were included in a clinical trial designed to support the safety of SUBSYS. Two of the nine subjects with mucositis (one with Grade 1 and one with Grade 2) reported a burning sensation in the oral mucosa after treatment. Both of these events were considered mild and probably related to treatment. There was no change in grade of mucositis after treatment for any subject.

6.2 Postmarketing Experience

The following adverse reactions have been identified during post approval use of fentanyl. Because these reactions are reported voluntarily from a population of uncertain size, it is not always possible to reliably estimate their frequency or establish a causal relationship to drug exposure.

Serotonin syndrome: Cases of serotonin syndrome, a potentially life-threatening condition, have been reported during concomitant use of opioids with serotonergic drugs.

Adrenal insufficiency: Cases of adrenal insufficiency have been reported with opioid use, more often following greater than one month of use.

Anaphylaxis: Anaphylaxis has been reported with ingredients contained in SUBSYS.

Androgen deficiency: Cases of androgen deficiency have occurred with chronic use of opioids [see Clinical Pharmacology (12.2)] .

7 DRUG INTERACTIONS

Table 6 includes clinically significant drug interactions with SUBSYS.

Table 6. Clinically Significant Drug Interactions with SUBSYS
Inhibitors of CYP3A4
Clinical Impact: | The concomitant use of SUBSYS and CYP3A4 inhibitors can increase the plasma concentration of fentanyl, resulting in increased or prolonged opioid effects, particularly when an inhibitor is added after a stable dose of SUBSYS is achieved [see Warnings and Precautions (5.3)] .; After stopping a CYP3A4 inhibitor, as the effects of the inhibitor decline, the fentanyl plasma concentration will decrease [see Clinical Pharmacology (12.3)] , resulting in decreased opioid efficacy or a withdrawal syndrome in patients who had developed physical dependence to fentanyl.
Intervention: | If concomitant use is necessary, consider dosage reduction of SUBSYS until stable drug effects are achieved. Monitor patients for respiratory depression and sedation at frequent intervals.; If a CYP3A4 inhibitor is discontinued, consider increasing the SUBSYS dosage until stable drug effects are achieved. Monitor for signs of opioid withdrawal.
Examples | Macrolide antibiotics (e.g., erythromycin), azole-antifungal agents (e.g. ketoconazole), protease inhibitors (e.g., ritonavir)
CYP3A4 Inducers
Clinical Impact: | The concomitant use of SUBSYS and CYP3A4 inducers can decrease the plasma concentration of fentanyl [see Clinical Pharmacology (12.3)] , resulting in decreased efficacy or onset of a withdrawal syndrome in patients who have developed physical dependence to fentanyl [see Warnings and Precautions (5.3)] .; After stopping a CYP3A4 inducer, as the effects of the inducer decline, the fentanyl plasma concentration will increase [see Clinical Pharmacology (12.3)] , which could increase or prolong both the therapeutic effects and adverse reactions, and may cause serious respiratory depression.
Intervention: | If concomitant use is necessary, consider increasing the SUBSYS dosage until stable drug effects are achieved. Monitor for signs of opioid withdrawal. If a CYP3A4 inducer is discontinued, consider SUBSYS dosage reduction and monitor for signs of respiratory depression.
Examples | Rifampin, carbamazepine, phenytoin
Benzodiazepines and other Central Nervous System (CNS) Depressants
Clinical Impact: | Due to additive pharmacologic effect, the concomitant use of benzodiazepines or other CNS depressants including alcohol, increases the risk of respiratory depression, profound sedation, coma, and death.
Intervention: | Reserve concomitant prescribing of these drugs for use in patients for whom alternative treatment options are inadequate. Limit dosages and durations to the minimum required. Follow patients closely for signs of respiratory depression and sedation [see Warnings and Precautions (5.1)] . If concomitant use is warranted, consider prescribing naloxone for the emergency treatment of opioid overdose [see Dosage and Administration (2.2), Warnings and Precautions (5.1, 5.4, 5.6)] .
Examples: | Benzodiazepines and other sedatives/hypnotics, anxiolytics, tranquilizers, muscle relaxants, general anesthetics, antipsychotics, other opioids, alcohol.
Serotonergic Drugs
Clinical Impact: | The concomitant use of opioids with other drugs that affect the serotonergic neurotransmitter system has resulted in serotonin syndrome [see Warnings and Precautions (5.10)] .
Intervention: | If concomitant use is warranted, carefully observe the patient, particularly during treatment initiation and dose adjustment. Discontinue SUBSYS if serotonin syndrome is suspected.
Examples: | Selective serotonin reuptake inhibitors (SSRIs), serotonin and norepinephrine reuptake inhibitors (SNRIs), tricyclic antidepressants (TCAs), triptans, 5-HT3 receptor antagonists, drugs that effect the serotonin neurotransmitter system (e.g., mirtazapine, trazodone, tramadol), certain muscle relaxants (i.e., cyclobenzaprine, metaxalone), monoamine oxidase (MAO) inhibitors (those intended to treat psychiatric disorders and also others, such as linezolid and intravenous methylene blue).
Monoamine Oxidase Inhibitors (MAOIs)
Clinical Impact: | MAOI interactions with opioids may manifest as serotonin syndrome [see Warnings and Precautions (5.10)] or opioid toxicity (e.g., respiratory depression, coma) [see Warnings and Precautions (5.2)] .
Intervention: | The use of SUBSYS is not recommended for patients taking MAOIs or within 14 days of stopping such treatment.
Examples: | phenelzine, tranylcypromine, linezolid
Mixed Agonist/Antagonist and Partial Agonist Opioid Analgesics
Clinical Impact: | May reduce the analgesic effect of SUBSYS and/or precipitate withdrawal symptoms.
Intervention: | Avoid concomitant use.
Examples: | butorphanol, nalbuphine, pentazocine, buprenorphine,
Muscle Relaxants
Clinical Impact: | Fentanyl may enhance the neuromuscular blocking action of skeletal muscle relaxants and produce an increased degree of respiratory depression.
Intervention: | Monitor patients for signs of respiratory depression that may be greater than otherwise expected and decrease the dosage of SUBSYS and/or the muscle relaxant as necessary. Due to the risk of respiratory depression with concomitant use of skeletal muscle relaxants and opioids, consider prescribing naloxone for the emergency treatment of opioid overdose [see Dosage and Administration (2.2), Warnings and Precautions (5.1, 5.4)]
Diuretics
Clinical Impact: | Opioids can reduce the efficacy of diuretics by inducing the release of antidiuretic hormone.
Intervention: | Monitor patients for signs of diminished diuresis and/or effects on blood pressure and increase the dosage of the diuretic as needed.
Anticholinergic Drugs
Clinical Impact: | The concomitant use of anticholinergic drugs may increase risk of urinary retention and/or severe constipation, which may lead to paralytic ileus.
Intervention: | Monitor patients for signs of urinary retention or reduced gastric motility when SUBSYS is used concomitantly with anticholinergic drugs.

8 USE IN SPECIFIC POPULATIONS

8.1 Pregnancy

Risk Summary

Prolonged use of opioid analgesics during pregnancy may cause neonatal opioid withdrawal syndrome [see Warnings and Precautions (5.8)] . Available data with SUBSYS in pregnant women are insufficient to inform a drug-associated risk for major birth defects and miscarriage.

In animal reproduction studies, fentanyl administration to pregnant rats during organogenesis was embryocidal at doses within the range of the human recommended dosing. When administered during gestation through lactation fentanyl administration to pregnant rats resulted in reduced pup survival at doses within the range of the human recommended dosing. No evidence of malformations was noted in animal studies completed to date [ see Data].

The estimated background risk of major birth defects and miscarriage for the indicated population is unknown. All pregnancies have a background risk of birth defect, loss, or other adverse outcomes. In the U.S. general population, the estimated background risk of major birth defects and miscarriage in clinically recognized pregnancies is 2-4% and 15-20%, respectively.

Clinical Considerations

Fetal/Neonatal Adverse Reactions

Prolonged use of opioid analgesics during pregnancy for medical or nonmedical purposes can result in physical dependence in the neonate and neonatal opioid withdrawal syndrome shortly after birth. Neonatal opioid withdrawal syndrome presents as irritability, hyperactivity and abnormal sleep pattern, high pitched cry, tremor, vomiting, diarrhea and failure to gain weight. The onset, duration, and severity of neonatal opioid withdrawal syndrome vary based on the specific opioid used, duration of use, timing and amount of last maternal use, and rate of elimination of the drug by the newborn. Observe newborns for symptoms of neonatal opioid withdrawal syndrome and manage accordingly [see Warnings and Precautions (5.8)] .

Labor or Delivery

Opioids cross the placenta and may produce respiratory depression and psycho-physiologic effects in neonates. An opioid antagonist, such as naloxone, must be available for reversal of opioid-induced respiratory depression in the neonate. SUBSYS is not recommended for use in pregnant women during or immediately prior to labor, when other analgesic techniques are more appropriate. Opioid analgesics, including SUBSYS, can prolong labor through actions which temporarily reduce the strength, duration, and frequency of uterine contractions. However, this effect is not consistent and may be offset by an increased rate of cervical dilation, which tends to shorten labor. Monitor neonates exposed to opioid analgesics during labor for signs of excess sedation and respiratory depression.

Data

Human Data

In women treated acutely with intravenous or epidural fentanyl during labor, symptoms of neonatal respiratory or neurological depression were no more frequent than would be expected in infants of untreated mothers.

Transient neonatal muscular rigidity has been observed in infants whose mothers were treated with intravenous fentanyl.

Animal Data

Fentanyl has been shown to embryocidal in pregnant rats at doses of 30 mcg/kg intravenously (0.4 times the 800 mcg dose of SUBSYS on a mg/m^2 basis) and 160 mcg/kg subcutaneously (2 times the 800 mcg dose of SUBSYS based on a mg/m^2 basis). There was no evidence of teratogenicity was reported.

No evidence of malformations or adverse effects on the fetus was reported in a published study in which pregnant rats were administered fentanyl continuously via subcutaneously implanted osmotic minipumps at doses of 10, 100, or 500 mcg/kg/day starting 2-weeks prior to breeding and throughout pregnancy. The high dose was approximately 6 times the human dose of 800 mcg SUBSYS per pain episode on a mg/m^2 basis and produced mean steady-state plasma levels that are 5.3 times higher than the mean Cmax observed following administration of 800 mcg dose of SUBSYS in humans.

8.2 Lactation

Risk Summary

Fentanyl is present in breast milk. One published lactation study reports a relative infant dose of fentanyl of 0.024%. However, there is insufficient information to determine the effects of fentanyl on the breastfed infant and the effects of fentanyl on milk production.

Because of the potential for serious adverse reactions, including excess sedation and respiratory depression in a breastfed infant, advise patients that breastfeeding is not recommended during treatment with SUBSYS.

Clinical Considerations

Monitor infants exposed to SUBSYS through breast milk for excess sedation and respiratory depression. Withdrawal symptoms can occur in breastfed infants when maternal administration of an opioid analgesic is stopped, or when breast-feeding is stopped.

8.3 Females and Males of Reproductive Potential

Infertility

Chronic use of opioids may cause reduced fertility in females and males of reproductive potential. It is not known whether these effects on fertility are reversible [see Adverse Reactions (6), Clinical Pharmacology (12.2), Nonclinical Toxicology (13.1)] .

8.4 Pediatric Use

Safety and efficacy in pediatric patients below the age of 18 years have not been established.

8.5 Geriatric Use

Of the 359 patients in clinical studies of SUBSYS in breakthrough cancer pain, 27% were 60 years of age and older, 17% were 65 years of age and older, and 3% were 75 years of age and older. No difference was noted in the safety profile of the group over 65 years of age as compared to younger patients in SUBSYS clinical trials.

Elderly patients have been shown to be more sensitive to the effects of fentanyl when administered intravenously, compared with the younger population. Therefore, monitor patients for respiratory depression and CNS effects when titrating SUBSYS in elderly patients.

Respiratory depression is the chief risk for elderly patients treated with opioids, and has occurred after large initial doses were administered to patients who were not opioid tolerant or when opioids were co-administered with other agents that depress respiration. Titrate the dosage of SUBSYS slowly in geriatric patients and monitor closely for signs of central nervous system and respiratory depression [ see Warnings and Precautions (5.1)] .

Fentanyl is known to be substantially excreted by the kidney, and the risk of adverse reactions to this drug may be greater in patients with impaired renal function. Because elderly patients are more likely to have decreased renal function, care should be taken in dose selection, and it may be useful to monitor renal function.

8.6 Patients with Renal or Hepatic Impairment

Insufficient information exists to make recommendations regarding the use of SUBSYS in patients with impaired renal or hepatic function. Fentanyl is metabolized primarily via the human CYP450 3A4 isoenzyme system and mostly eliminated in urine. If the drug is used in these patients, monitor patients closely for signs of respiratory and central nervous system depression.

8.7 Sex

Both male and female opioid tolerant patients with cancer were studied for the treatment of breakthrough cancer pain. No clinically relevant sex differences were noted either in dosage requirement or in observed adverse reactions.

9 DRUG ABUSE AND DEPENDENCE

9.1 Controlled Substance

SUBSYS contains fentanyl a Schedule II controlled substance.

9.2 Abuse

SUBSYS contains fentanyl, a substance with a high potential for abuse similar to other opioids including hydrocodone, hydromorphone, methadone, morphine, oxycodone, oxymorphone, and tapentadol. SUBSYS can be abused and is subject to misuse, addiction, and criminal diversion [ see Warnings and Precautions (5.6)] .

All patients treated with opioids require careful monitoring for signs of abuse and addiction, because use of opioid analgesic products carries the risk of addiction even under appropriate medical use.

Prescription drug abuse is the intentional non-therapeutic use of a prescription drug, even once, for its rewarding psychological or physiological effects.

Drug addiction is a cluster of behavioral, cognitive, and physiological phenomena that develop after repeated substance use and includes: a strong desire to take the drug, difficulties in controlling its use, persisting in its use despite harmful consequences, a higher priority given to drug use than to other activities and obligations, increased tolerance, and sometimes a physical withdrawal.

“Drug-seeking” behavior is very common in persons with substance use disorders. Drug-seeking tactics include emergency calls or visits near the end of office hours, refusal to undergo appropriate examination, testing, or referral, repeated “loss” of prescriptions, tampering with prescriptions, and reluctance to provide prior medical records or contact information for other treating health care provider(s). “Doctor shopping” (visiting multiple prescribers to obtain additional prescriptions) is common among drug abusers and people suffering from untreated addiction. Preoccupation with achieving adequate pain relief can be appropriate behavior in a patient with poor pain control.

Abuse and addiction are separate and distinct from physical dependence and tolerance. Health care providers should be aware that addiction may not be accompanied by concurrent tolerance and symptoms of physical dependence in all addicts. In addition, abuse of opioids can occur in the absence of true addiction.

SUBSYS, like other opioids, can be diverted for non-medical use into illicit channels of distribution. Careful record-keeping of prescribing information, including quantity, frequency, and renewal requests, as required by state and federal law, is strongly advised.

Proper assessment of the patient, proper prescribing practices, periodic re-evaluation of therapy, and proper dispensing and storage are appropriate measures that help to limit abuse of opioid drugs.

Risks Specific to the Abuse of SUBSYS

SUBSYS is for sublingual transmucosal use only. Abuse of SUBSYS poses a risk of overdose and death. The risk is increased with concurrent abuse of SUBSYS with alcohol and other central nervous system depressants.

9.3 Dependence

Both tolerance and physical dependence can develop during chronic opioid therapy. Tolerance is the need for increasing doses of opioids to maintain a defined effect such as analgesia (in the absence of disease progression or other external factors). Tolerance may occur to both the desired and undesired effects of drugs, and may develop at different rates for different effects.

Physical dependence results in withdrawal symptoms after abrupt discontinuation or a significant dosage reduction of a drug. Withdrawal also may be precipitated through the administration of drugs with opioid antagonist activity (e.g., naloxone, nalmefene), mixed agonist/antagonist analgesics (e.g., pentazocine, butorphanol, nalbuphine), or partial agonists (e.g., buprenorphine). Physical dependence may not occur to a clinically significant degree until after several days to weeks of continued opioid usage.

Infants born to mothers physically dependent on opioids will also be physically dependent and may exhibit respiratory difficulties and withdrawal signs [ see Use in Specific Populations (8.1)] .

10 OVERDOSAGE

Clinical Presentation

Acute overdose with SUBSYS be manifested by respiratory depression, somnolence progressing to stupor or coma, skeletal muscle flaccidity, cold and clammy skin, constricted pupils, and, in some cases, pulmonary edema, bradycardia, hypotension, partial or complete airway obstruction, atypical snoring, and death. Marked mydriasis rather than miosis may be seen with hypoxia in overdose situations [ see Clinical Pharmacology (12.2)] .

Treatment of Overdose

In case of overdose, priorities are the reestablishment of a patent and protected airway and institution of assisted or controlled ventilation, if needed. Employ other supportive measures (including oxygen and vasopressors) in the management of circulatory shock and pulmonary edema as indicated. Cardiac arrest or arrhythmias will require advanced life-support techniques.

The opioid antagonists, naloxone or nalmefene, are specific antidotes to respiratory depression resulting from opioid overdose. For clinically significant respiratory or circulatory depression secondary to fentanyl overdose, administer an opioid antagonist. Opioid antagonists should not be administered in the absence of clinically significant respiratory or circulatory depression secondary to fentanyl overdose.

Because the duration of opioid reversal is expected to be less than the duration of action of fentanyl in SUBSYS, carefully monitor the patient until spontaneous respiration is reliably re-established. If the response to an opioid antagonist is suboptimal or only brief in nature, administer additional antagonist as directed by the product’s prescribing information.

In an individual physically dependent on opioids, administration of the recommended usual dosage of the antagonist will precipitate an acute withdrawal syndrome. The severity of the withdrawal symptoms experienced will depend on the degree of physical dependence and the dose of the antagonist administered. If a decision is made to treat serious respiratory depression in the physically dependent patient, administration of the antagonist should be begun with care and by titration with smaller than usual doses of the antagonist.

11 DESCRIPTION

SUBSYS (fentanyl sublingual spray) is an opioid agonist, available as a sublingual spray designed to deliver doses of 100, 200, 400, 600, 800, 1200 and 1600 mcg of fentanyl. The chemical name of fentanyl is N-phenyl-N-[1-(2-phenylethyl)-4-piperidinyl]propanamide.

Fentanyl is a highly lipophilic compound (octanol-water partition coefficient at pH 7.4 is 860:1) that is freely soluble in ethanol and methanol and practically insoluble in water (1:40). The molecular weight of the free base is 336.47. The pKa is 8.4.

The inactive ingredients in SUBSYS include: dehydrated alcohol 63.6% (V/V), purified water, propylene glycol, xylitol, and L-menthol.

12 CLINICAL PHARMACOLOGY

12.1 Mechanism of Action

Fentanyl is an opioid agonist whose principal therapeutic action is analgesia.

12.2 Pharmacodynamics

Effects on the Central Nervous System

Fentanyl produces respiratory depression by direct action on brain stem respiratory centers. The respiratory depression involves both a reduction in the responsiveness of the brain stem respiratory centers to increases in carbon dioxide tension and to electrical stimulation.

Fentanyl causes miosis, even in total darkness. Pinpoint pupils are a sign of opioid overdose but are not pathognomonic (e.g., pontine lesions of hemorrhagic or ischemic origins may produce similar findings). Marked mydriasis rather than miosis may be seen due to hypoxia in overdose situations.

Effects on the Gastrointestinal Tract and Other Smooth Muscle

Fentanyl causes a reduction in motility associated with an increase in smooth muscle tone in the antrum of the stomach and duodenum. Digestion of food in the small intestine is delayed and propulsive contractions are decreased. Propulsive peristaltic waves in the colon are decreased, while tone may be increased to the point of spasm resulting in constipation. Other opioid-induced effects may include a reduction in biliary and pancreatic secretions, spasm of sphincter of Oddi, and transient elevations in serum amylase.

Effects on the Cardiovascular System

Fentanyl produces peripheral vasodilation which may result in orthostatic hypotension or syncope. Manifestations of histamine release and/or peripheral vasodilation may include pruritus, flushing, red eyes and sweating and/or orthostatic hypotension.

Effects on the Endocrine System

Opioids inhibit the secretion of adrenocorticotropic hormone (ACTH), cortisol, and luteinizing hormone (LH) in humans [see Adverse Reactions (6.2)] . They also stimulate prolactin, growth hormone (GH) secretion, and pancreatic secretion of insulin and glucagon.

Chronic use of opioids may influence the hypothalamic-pituitary-gonadal axis, leading to androgen deficiency that may manifest as low libido, impotence, erectile dysfunction, amenorrhea, or infertility. The causal role of opioids in the clinical syndrome of hypogonadism is unknown because the various medical, physical, lifestyle, and psychological stressors that may influence gonadal hormone levels have not been adequately controlled for in studies conducted to date [see Adverse Reactions (6.2)] .

Effects on the Immune System

Opioids have been shown to have a variety of effects on components of the immune system in in vitro and animal models. The clinical significance of these findings is unknown. Overall, the effects of opioids appear to be modestly immunosuppressive.

Concentration–Efficacy Relationships

The analgesic effects of fentanyl are related to the blood level of the drug, if proper allowance is made for the delay into and out of the CNS (a process with a 3- to 5-minute half-life).

In general, the effective concentration and the concentration at which toxicity occurs increase with increasing tolerance with any and all opioids. The rate of development of tolerance varies widely among individuals. The minimum effective analgesic concentration of fentanyl for any individual patient may increase over time due to an increase in pain, the development of a new pain syndrome, and/or the development of analgesic tolerance.

Concentration–Adverse Reaction Relationships

There is a relationship between increasing fentanyl plasma concentration and increasing frequency of dose-related opioid adverse reactions such as nausea, vomiting, CNS effects, and respiratory depression. In opioid-tolerant patients, the situation may be altered by the development of tolerance to opioid-related adverse reactions [see Dosage and Administration (2.1, 2.3, 2.5)] .

Respiratory System

All opioid mu-receptor agonists, including fentanyl, produce dose-dependent respiratory depression. The risk of respiratory depression is less in patients receiving chronic opioid therapy who develop tolerance to respiratory depression and other opioid effects. Peak respiratory depressive effects may be seen as early as 15 to 30 minutes from the start of oral transmucosal fentanyl citrate product administration and may persist for several hours.

Serious or fatal respiratory depression can occur even at recommended doses. Although not observed with oral transmucosal fentanyl products in clinical trials, fentanyl given rapidly by intravenous injection in large doses may interfere with respiration by causing rigidity in the muscles of respiration [see Warnings and Precautions (5.1)].

12.3 Pharmacokinetics

Absorption

Following the single dose administration of SUBSYS, 400 mcg, the mean absolute bioavailability of fentanyl is 76% as measured by AUC0-∞. Fentanyl pharmacokinetic profile and bioavailability depend on the fraction of the dose that is absorbed through the sublingual mucosa and the fraction swallowed from the gastrointestinal tract.

In a study that compared the relative bioavailability of SUBSYS and oral transmucosal fentanyl citrate [OTFC]) in 21 healthy adult subjects, the rate and extent of fentanyl absorption were considerably greater with SUBSYS [34% greater maximum plasma concentration (Cmax) and 38% greater systemic exposure (AUCinf)] (Table 7 and Figure 1) [see Dosage and Administration (2.1, 2.3, 2.5) and Warnings and Precautions (5.5)] .

Figure 1 includes an inset which shows the mean plasma concentration versus time profile to 4 hours.

Table 7. Pharmacokinetic Parameters of Fentanyl in Healthy Adult Subjects Receiving a Single Dose of SUBSYS or OTFC
Pharmacokinetic Parameter (Mean (CV%)) | SUBSYS 400 mcg | OTFC 400 mcg
Tmax (hour)* | 1.5 (0.17, 2.00) | 2.0 (0.5, 2.12)
Cmax (ng/mL) | 0.813 (31.00) | 0.607 (30.48)
AUC0-t (ng/mL × hr) | 4.863 (35.12) | 3.677 (39.16)
AUC0-∞ (ng/mL × hr) | 5.761 (33.26) | 4.182 (39.93)
* Data for Tmax presented as median (range)

Figure 1 Mean Fentanyl Plasma Concentration-Time Profiles Following Single Dose Administration of SUBSYS 400 mcg and OTFC 400 mcg in Healthy Adult Subjects

Neither peak fentanyl concentration nor total exposure was appreciably affected by the pretreatment of oral cavity with hot water or refrigerated iced water, low or high pH beverages when SUBSYS was administered under fasted condition.

Dose proportionality among the five available strengths of SUBSYS (100, 200, 400, 600, and 800 mcg) has been evaluated in a crossover study in healthy subjects. Mean plasma fentanyl levels following these five dose levels of SUBSYS are shown in Figure 2. The curves for each dose level are similar in shape with increasing dose levels producing increasing plasma fentanyl levels. The Cmax and AUC0-∞ values increased in a dose-dependent manner that is approximately proportional to the SUBSYS doses administered.

Figure 2. Mean Fentanyl Plasma Concentration-Time Profiles (36 hours) after Administration of SUBSYS 100 mcg, 200 mcg, 400 mcg, 600 mcg, and 800 mcg in Healthy Subjects

The pharmacokinetic parameters of the five strengths of SUBSYS tested are shown in Table 8. The mean Cmax ranged from 0.202 – 1.610 ng/mL. The median time of maximum plasma concentration (Tmax) across these five doses of SUBSYS varied from 0.67 - 1.25 hours (range of 0.08 – 4.00 hours) as measured after the start of administration.

Table 8. Fentanyl Plasma Pharmacokinetic Parameters in Healthy Adult Subjects Receiving Single Doses of 100, 200, 400, 600, 800 mcg of SUBSYS
Pharmacokinetic Parameter (Mean (%CV)) | 100 mcg | 200 mcg | 400 mcg | 600 mcg | 800 mcg
Tmax (hr)* | 1.25 (0.17-2.05) | 1.25 (0.17-2.03) | 1.00 (0.17-2.03) | 0.67 (0.08-2.00) | 0.69 (0.17-4.00)
Cmax (ng/mL) | 0.202 (28.35) | 0.378 (29.69) | 0.800 (27.66) | 1.17 (32.48) | 1.610 (37.22)
AUClast (ng/mL × hr) | 0.9776 (49.82) | 1.985 (40.93) | 4.643 (44.53) | 6.682 (32.46) | 9.450 (36.62)
AUC0-∞ (ng/mL × hr) | 1.245 (53.82) | 2.475 (46.48) | 5.342 (44.16) | 7.446 (81.54) | 10.38 (35.60)
T½ (hr) | 5.25 (89.92) | 8.45 (77.94) | 11.03 (62.20) | 10.64 (41.73) | 11.99 (32.15)
* Data for Tmax presented as median (range)

Distribution
Fentanyl is highly lipophilic. Animal data showed that following absorption, fentanyl is rapidly distributed to the brain, heart, lungs, kidneys and spleen followed by a slower redistribution to muscles and fat. The plasma protein binding of fentanyl is 80-85%. The main binding protein is alpha-1-acid glycoprotein, but both albumin and lipoproteins contribute to some extent. The free fraction of fentanyl increases with acidosis. The mean volume of distribution at steady state (Vss) was 4 L/kg.

Elimination

Metabolism
Fentanyl is metabolized in the liver and in the intestinal mucosa to norfentanyl by cytochrome P450 3A4 isoform. Norfentanyl was not found to be pharmacologically active in animal studies [see Drug Interactions (7)] .

Excretion
Fentanyl is primarily (more than 90%) eliminated by biotransformation to N-dealkylated and hydroxylated inactive metabolites. Less than 7% of the dose is excreted unchanged in the urine, and only about 1% is excreted unchanged in the feces. The metabolites are mainly excreted in the urine, while fecal excretion is less important. The total plasma clearance of fentanyl was 0.5 L/hr/kg (range 0.3 - 0.7 L/hr/kg). The terminal half-life after SUBSYS administration is from 5 to 12 hours.

Specific Population

Patients with mucositis:

The effect of mucositis (Grades 1 and 2) on the pharmacokinetics of SUBSYS was studied in a group of cancer patients with mucositis (N = 7 for Grade 1 and N = 2 for Grade 2) and without mucositis (N = 8). A single 100 mcg dose was administered. Mean summary statistics (standard deviation in parentheses) for patients with Grade 1 mucositis and patients without mucositis are presented in Table 9. Cancer patients with Grade 1 mucositis exhibited 73% greater Cmax and 52% greater AUClast values in comparison to patients without mucositis. The two cancer patients with Grade 2 mucositis had 4- and 7-fold higher Cmax and ≥3- fold higher AUClast values compared to patients without mucositis.

Monitor patients with Grade 1 mucositis closely for signs of respiratory and central nervous system depression particularly during initiation of therapy with SUBSYS. As a result of the large and variable increase in exposure of fentanyl, use of SUBSYS should be avoided in patients with Grade 2 and more severe mucositis unless the benefits are expected to outweigh the risk of respiratory depression.

Table 9. Mean (%CV) Pharmacokinetic Parameters in Patients with Mucositis
Patient Status | N | Cmax (ng/mL) | Tmax (hr)* | AUC0-last (ng/mL × hr)
Mucositis Grade 1 | 7 | 0.45 (95.56) | 0.25 (0.25, 2.00) | 1.38 (44.93)
No Mucositis | 8 | 0.26 (57.69) | 0.38 (0.25, 2.00) | 0.91 (14.29)
* Data for Tmax presented as median (range)

13 NONCLINICAL TOXICOLOGY

13.1 Carcinogenesis, Mutagenesis, Impairment of Fertility

Carcinogenesis
Long-term studies in animals to evaluate the carcinogenic potential of fentanyl have not been conducted

Mutagenesis
Fentanyl citrate was not mutagenic in the in vitro Ames reverse mutation assay in S. typhimurium or E. coli or the mouse lymphoma mutagenesis assay, and was not clastogenic in the in vivo mouse micronucleus assay.

Impairment of Fertility
Fentanyl has been shown to impair fertility in rats at doses of 30 mcg/kg intravenously and 160 mcg/kg subcutaneously. Conversion to the human equivalent doses indicates that this is within the range of the human recommended dosing for SUBSYS.

14 CLINICAL STUDIES

The efficacy of SUBSYS was demonstrated in a double-blind, placebo-controlled, crossover study in opioid tolerant adult patients with cancer and breakthrough pain. The dose range studied was from 100 mcg per dose to 1600 mcg per dose. Patients entering the trial must have had on average 1-4 episodes of pain per day not controlled on stable, chronic maintenance doses of opioid medication of at least 60 mg/day of morphine, 25 mcg/hr of transdermal fentanyl, or an equianalgesic dose of another opioid for at least 7 days.

The study began with an open-label dose titration period followed by a double-blind treatment period. The goal of titration was to find the dose of SUBSYS that provided adequate analgesia with acceptable side effects. Patients were titrated from a 100 mcg starting dose. Once a successful dose was established, patients were enrolled into the double-blind period and randomized to a sequence of 10 treatments; 7 with SUBSYS and 3 with placebo.

Patients assessed pain intensity on a 100 mm visual analog scale that rated the pain as 0=none to 100=worst possible pain. With each episode of breakthrough pain, pain intensity was assessed first and then treatment was administered. Pain intensity (0-100) was then measured at 5, 10, 15, 30, 45 and 60 minutes after the start of administration. The summed pain intensity difference from baseline to 30 minutes after dosing was the primary efficacy measure.

Out of 130 patients who entered the titration phase, 98 (75%) were able to titrate to a dose that adequately reduced pain with tolerable side effects and entered into the double-blind period.

The breakdown of successful dose for the patients entering the double-blind period of the study is as follows:

SUBSYS Dose | Total No. (%) n=96
100 mcg | 4 (4%)
200 mcg | 7 (7%)
400 mcg | 14 (15%)
600 mcg | 15 (16%)
800 mcg | 23 (24%)
1200 mcg (2 × 600 mcg) | 20 (21%)
1600 mcg (2 × 800 mcg) | 13 (14%)

SUBSYS produced a statistically significantly greater reduction in pain intensity compared to placebo as measured by the Summed Pain Intensity Differences scale (SPID) at 30 minutes.

The primary outcome measure, the mean sum of the pain intensity difference at 30 minutes (SPID30), was statistically significantly higher for SUBSYS than for placebo. The difference in mean pain intensity based on a 100 mm visual analog scale is displayed in Figure 3.

Figure 3. Pain Intensity Differences over Time

16 HOW SUPPLIED/STORAGE AND HANDLING

SUBSYS (fentanyl sublingual spray) is supplied as spray units.

Each SUBSYS carton contains individual blister packages containing spray units of SUBSYS, a supply of small white disposal bags for disposing of used SUBSYS units and charcoal-lined disposal pouches, a supply of charcoal-lined disposal pouches (wrapped in aluminum foil) for use when disposing of the contents of unused SUBSYS units, a Medication Guide and a Package Insert.

SUBSYS is supplied in individually sealed, protective blister packages. These blister packages are packed into 10 and 30 per shelf cartons.

Each unit dose system consists of a white actuator attached to a light purple vial holder. The dosage strength is marked on the label on the actuator, the blister package and the shelf carton. See the protective blister package and shelf carton for product information.

Dosage Strength (fentanyl base) | Carton/Blister Package Color | NDC Number
100 mcg | Blue | 20482-001-01
100 mcg | Blue | 20482-001-10
200 mcg | Green | 20482-002-01
200 mcg | Green | 20482-002-10
400 mcg | Magenta (Pink) | 20482-004-01
400 mcg | Magenta (Pink) | 20482-004-10
600 mcg | Purple | 20482-006-01
600 mcg | Purple | 20482-006-10
800 mcg | Orange | 20482-008-01
800 mcg | Orange | 20482-008-10
1200 mcg | Brown | 20482-012-01
1200 mcg | Brown | 20482-012-15
1600 mcg | Red | 20482-016-01
1600 mcg | Red | 20482-016-15

Note: Colors are a secondary aid in product identification. Please be sure to confirm the printed dosage before dispensing.

Storage and Handling

Store at 20-25ºC (68-77ºF) with excursions permitted between 15º and 30ºC (59º to 86ºF) until ready to use. [See USP Controlled Room Temperature.] Do not use if the blister package has been opened.

Store SUBSYS securely and dispose of properly [see Patient Counseling Information (17)].

17 PATIENT COUNSELING INFORMATION

Advise the patient to read the FDA-approved patient labeling (Medication Guide).

Storage and Disposal of Unused and Used SUBSYS [see Instructions for Use].

Because of risk associated with accidental ingestion, misuse, and abuse, advise patients to store SUBSYS securely, out of sight and reach of children and in a location not accessible by others, including visitors to the home [see Warnings and Precautions (5.1, 5.2), Drug Abuse and Dependence (9.2)]. Inform Patients that leaving SUBSYS unsecured can pose a deadly risk to others in the home.

Advise patients and caregivers that when medicines are no longer needed, they should be disposed of promptly.

Disposal of Unopened SUBSYS Unit Dose Systems When No Longer Needed

Patients and members of their household must be advised to dispose of any unopened units remaining from a prescription as soon as they are no longer needed.

To dispose of the unopened SUBSYS units:

1. Using a pair of scissors, cut the blister package on the line marked by an image of a pair of scissors and the instruction “cut to open” printed on the blister. Peel back the blister material to remove the SUBSYS unit from the package.

2. Remove a charcoal-lined disposal pouch from the aluminum foil package by tearing open the package at the notch.

3. Hold the charcoal-lined disposal pouch with the opening facing up. Put the nozzle of the SUBSYS spray unit upside-down into the opening of the charcoal-lined disposal pouch.

4. Squeeze your fingers and thumb together to spray SUBSYS into the charcoal-lined disposal pouch.

5. Dispose of the empty spray unit in a disposal bag.

6. Repeat the above steps for each unused SUBSYS spray unit. The charcoal-lined disposal pouch may be used for disposing of the contents of up to 10 spray units. Make sure all unused spray units have been sprayed into a charcoal-lined disposal pouch.

7. To seal a used charcoal-lined disposal pouch, remove the backing from the adhesive strip. Fold the flap down and press to seal the charcoal-lined disposal pouch.

8. Place the sealed charcoal-lined disposal pouch into a disposal bag.

9. To seal the disposal bag, remove the backing from the adhesive strip. Fold the flap down and press to seal.

10. Discard the sealed disposal bag in the trash out of the reach of children.

Disposal of Used SUBSYS Unit Dose Systems

Patients must be instructed to safely dispose of used SUBSYS units.

1. After administration of SUBSYS, place the used spray unit into one of the disposable bags provided with your prescription.

2. Seal the bag and discard into a trash container out of the reach of children.

Detailed instructions for the proper storage, administration, disposal, and important instructions for managing an overdose of SUBSYS are provided in the SUBSYS Medication Guide. Encourage patients to read this information in its entirety and give them an opportunity to have their questions answered.

In the event that a caregiver requires additional assistance in disposing of excess unusable units that remain in the home after a patient has expired, instruct them to call the toll-free number for West Therapeutic Development, LLC., 1-844-452-9263) or seek assistance from their local DEA office.

Life-Threatening Respiratory Depression
Inform patients of the risk of life-threatening respiratory depression, including information that the risk is greatest when starting SUBSYS or when the dosage is increased, and that it can occur even at recommended dosages.

Educate patients and caregivers on how to recognize respiratory depression and emphasize the importance of calling 911 or getting emergency medical help right away in the event of a known or suspected overdose [see Warnings and Precautions (5.1)] .

Patient Access to Naloxone for the Emergency Treatment of Opioid Overdose

Discuss with the patient and caregiver the availability of naloxone for the emergency treatment of opioid overdose, both when initiating and renewing treatment with SUBSYS. Inform patients and caregivers about the various ways to obtain naloxone as permitted by individual state naloxone dispensing and

prescribing requirements or guidelines (e.g., by prescription, directly from a pharmacist, or as part of a community-based program) [see Dosage and Administration (2.2), Warnings and Precautions (5.1)] .

Educate patients and caregivers on how to recognize the signs and symptoms of an overdose.

Explain to patients and caregivers that naloxone’s effects are temporary, and that they must call 911 or get emergency medical help right away in all cases of known or suspected opioid overdose, even if naloxone is administered [see Overdosage (10)] .

If naloxone is prescribed, also advise patients and caregivers:

- How to treat with naloxone in the event of an opioid overdose
- To tell family and friends about their naloxone and to keep it in a place where family and friends can access it in an emergency
- To read the Patient Information (or other educational material) that will come with their naloxone. Emphasize the importance of doing this before an opioid emergency happens, so the patient and caregiver will know what to do.

Increased Risk of Overdose and Death in Children Due to Accidental Exposure [see Warnings and Precautions (5.2)]

- Healthcare providers and dispensing pharmacists must specifically question patients or caregivers about the presence of children in the home (on a full time or visiting basis) and counsel them regarding the dangers to children from inadvertent exposure.
- Inform patients that accidental exposure, especially in children, may result in respiratory depression or death.
- Instruct patients to take steps to store SUBSYS securely and use the Child Safety Kit to store SUBSYS and other medicines out of the reach of children and to dispose of unused SUBYS by emptying all of the medicine into the charcoal-lined disposal pouch, seal the pouch, and dispose in the trash out of reach of children.
- Instruct patients and caregivers to keep both used and unused SUBSYS out of the reach of children.

SUBSYS Child Safety Kit
Provide patients and their caregivers with a SUBSYS Child Safety Kit. The kit consists of a portable carrying case, a lock for the bag and contains a package of cabinet and drawer child safety latches for securing the storage space at home to help patients store SUBSYS and other medicines out of the reach of children. To obtain a supply of Child Safety Kits, health care professionals can call West Therapeutic Development, LLC., at 1-844-452-9263.

Interactions with Benzodiazepines and Other CNS Depressants
Inform patients and caregivers that potentially fatal additive effects may occur if SUBSYS is used with benzodiazepines or other CNS depressants, including alcohol, and not to use these concomitantly unless supervised by a healthcare provider [see Warnings and Precautions (5.4), Drug Interactions (7)].

Addiction, Abuse, and Misuse
Inform patients that the use of SUBSYS, even when taken as recommended, can result in addiction, abuse, and misuse, which can lead to overdose and death [see Warnings and Precautions (5.6)]. Instruct patients not to share SUBSYS with others and to take steps to protect SUBSYS from theft or misuse.

Transmucosal Immediate-Release Fentanyl (TIRF) REMS

SUBSYS is available only through a restricted program called the Transmucosal Immediate Release Fentanyl (TIRF) REMS [see Warnings and Precautions (5.7)] . Inform the patient of the following notable requirements:

- Outpatients must be enrolled in the REMS program
- Patients must be opioid-tolerant to receive SUBSYS

SUBSYS is available only from certified pharmacies participating in this program. Therefore, provide patients with the telephone number and website for information on how to obtain the product.

Pharmacies, outpatients, and healthcare professionals who prescribe to outpatients are required to enroll in the program. Inpatient pharmacies must develop policies and procedures to verify opioid tolerance in inpatients who require SUBSYS while hospitalized [see Warnings and Precautions (5.7)].

Serotonin Syndrome
Inform patients that opioids could cause a rare but potentially life-threatening condition resulting from concomitant administration of serotonergic drugs. Warn patients of the symptoms of serotonin syndrome and to seek medical attention right away if symptoms develop. Instruct patients to inform their physicians if they are taking, or plan to take serotonergic medications. [see Warnings and Precautions (5.10), Drug Interactions (7)] .

MAOI Interaction
Inform patients to avoid taking SUBSYS while using any drugs that inhibit monoamine oxidase. Patients should not start MAOIs while taking SUBSYS [see Warnings and Precautions (5.1, 5.10); Drug Interactions (7)].

Adrenal Insufficiency
Inform patients that opioids could cause adrenal insufficiency, a potentially life-threatening condition. Adrenal insufficiency may present with non-specific symptoms and signs such as nausea, vomiting, anorexia, fatigue, weakness, dizziness, and low blood pressure. Advise patients to seek medical attention if they experience a constellation of these symptoms [see Warnings and Precautions (5.11)] .

Important Administration Instructions [see Dosage and Administration (2)]

- Instruct patients not to take SUBSYS for acute pain, postoperative pain, pain from injuries, headache, migraine or any other short-term pain, even if they have taken other opioid analgesics for these conditions.
- Instruct patients on the meaning of opioid tolerance and that SUBSYS is only to be used as a supplemental pain medication for patients with pain requiring around-the-clock opioids, who have developed tolerance to the opioid medication, and who need additional opioid treatment of breakthrough pain episodes.
- Instruct patients that, if they are not taking an opioid medication on a scheduled basis (around-the-clock), they should not take SUBSYS.
- Instruct patients that, if the breakthrough pain episode is not relieved 30 minutes after administration, they may take only one additional dose of SUBSYS using the same strength for that episode. Thus, patients should take no more than two doses of SUBSYS for any breakthrough pain episode.
- Instruct patients that they MUST wait at least 4 hours before treating another episode of breakthrough pain with SUBSYS.
- Instruct patients NOT to share SUBSYS and that sharing SUBSYS with anyone else could result in the other individual’s death due to overdose.
- Make patients aware that SUBSYS contains fentanyl which is a strong pain medication similar to hydromorphone, methadone, morphine, oxycodone, and oxymorphone.
- Instruct patients to talk to their doctor if breakthrough pain is not alleviated or worsens after taking SUBSYS.
- Instruct patients to use SUBSYS exactly as prescribed by their doctor and not to take SUBSYS more often than prescribed.
- Provide patients and their caregivers with a Medication Guide each time SUBSYS is dispensed because new information may be available.

Hypotension
Inform patients that SUBSYS may cause orthostatic hypotension and syncope. Instruct patients how to recognize symptoms of low blood pressure and how to reduce the risk of serious consequences should hypotension occur (e.g., sit or lie down, carefully rise from a sitting or lying position) [see Warnings and Precautions (5.12)] .

Anaphylaxis
Inform patients that anaphylaxis have been reported with ingredients contained in SUBSYS. Advise patients how to recognize such a reaction and when to seek medical attention [see Contraindications (4), Adverse Reactions (6)].

Pregnancy

Neonatal Opioid Withdrawal Syndrome
Inform patients that prolonged use of SUBSYS during pregnancy can result in neonatal opioid withdrawal syndrome, which may be life-threatening if not recognized and treated [See Warnings and Precautions (5.8), Use in Specific Populations (8.1)] .

Embryo-Fetal Toxicity
Inform female patients of reproductive potential that SUBSYS can (or may) cause fetal harm and to inform the healthcare provider of a known or suspected pregnancy [see Use in Specific Populations (8.1), Non-Clinical Toxicology (13.1)].

Lactation
Advise nursing mothers to monitor infants for increased sleepiness (more than usual), breathing difficulties, or limpness. Instruct nursing mothers to seek immediate medical care if they notice these signs [see Use in Specific Populations (8.2)] .

Infertility
Inform patients that chronic use of opioids may cause reduced fertility. It is not known whether these effects on fertility are reversible [see Adverse Reactions (6.2), Use in Specific Populations (8.3)].

Driving or Operating Heavy Machinery
Inform patients that SUBSYS may impair the ability to perform potentially hazardous activities such as driving a car or operating heavy machinery. Advise patients not to perform such tasks until they know how they will react to the medication [see Warnings and Precautions (5.16)] .

Constipation
Advise patients of the potential for severe constipation, including management instructions, and when to seek medical attention [see Adverse Reactions (6), Clinical Pharmacology (12.2)] .

Manufactured by:
Renaissance Lakewood, LLC, Lakewood, NJ 08701

Manufactured for and Distributed by:
West Therapeutic Development, LLC., Northbrook, IL 60062

U.S. Patents: 8,486,972 B2 and 8,486,973 B2

2104221

April 2021

SUBSYS® is a registered trademark of West Therapeutic Development, LLC

Medication Guide
SUBSYS® (sub sis))
(fentanyl) sublingual spray , CII

Important information about SUBSYS:
Do not use SUBSYS unless you are regularly using another opioid pain medicine around-the-clock for at least one week or longer for your cancer pain and your body is used to these medicines (this means that you are opioid tolerant). You can ask your healthcare provider if you are opioid tolerant.
Keep SUBSYS in a safe place away from children.
Get emergency help right away if:

- A child uses SUBSYS. SUBSYS can cause an overdose and death in any child who uses it.
- An adult who has not been prescribed SUSBYS uses it
- An adult who is not already taking opioids around-the-clock, uses SUBSYS

These are medical emergencies that can cause death.

SUBSYS is:

- A strong prescription pain medicine that contains an opioid (narcotic) that is used to manage breakthrough pain in adults (18 years of age and older) with cancer who are already routinely taking other opioid pain medicines around-the-clock for cancer pain. SUBSYS is started only after you have been taking other opioid pain medicines and your body has become used to them (you are opioid tolerant). Do not use SUBSYS if you are not opioid tolerant.
- An opioid pain medicine that can put you at risk for overdose and death. Even if you take your dose correctly as prescribed you are at risk for opioid addiction, abuse, and misuse that can lead to death.

Important information about SUBSYS:

- Get emergency help right away if you take too much SUBSYS (overdose) When you first start taking SUBSYS, when your dose is changed, or if you take too much (overdose), serious or life-threatening breathing problems that can lead to death may occur.
- Taking SUBSYS with other opioid medicines, that may make you sleepy, such as other pain medicines, anti-depressants, sleeping pills, anti-anxiety medicines, antihistamines, or tranquilizers, or with alcohol or street drugs can cause severe drowsiness, confusion, breathing problems, coma, and death.
- If you stop taking your around-the-clock opioid pain medicine for your cancer pain, you must stop using SUBSYS. You may no longer be opioid tolerant. Talk to your healthcare provider about how to treat your pain
- Never give anyone else your SUBSYS. They could die from taking it. Selling or giving away SUBSYS is against the law.
- Store SUBSYS securely, out of sight and reach of children, in a location not accessible by others, including visitors to the home.
- SUBSYS is available only through a program called the Transmucosal Immediate Release Fentanyl (TIRF) Risk Evaluation and Mitigation Strategy (REMS) Access program. To receive SUBSYS, you must:
  - talk to your healthcare provider
  - understand the benefits and risks of SUBSYS
  - agree to all of the instructions
  - sign the Patient-Prescriber Agreement form
- SUBSYS is only available at pharmacies that are part of the TIRF REMS Access program. Your healthcare provider will let you know the pharmacy closest to your home where you can have your SUBSYS prescription filled.
- Be very careful about taking other medicines that may make you sleepy, such as other pain medicines, anti-depressants, sleeping pills, anti-anxiety medicines, antihistamines, or tranquilizers.
- Know the medicines you take. Keep a list of them to show your healthcare provider and pharmacist when you get a new medicine.

Do not take SUBSYS if:

- You are not opioid tolerant. Opioid tolerant means that you are already taking other opioid pain medicines around-the-clock for your cancer pain, and your body is used to these medicines.
- You have severe asthma, trouble breathing, or other lung problems.
- You have a bowel blockage or have narrowing of the stomach or intestines
- You have a short-term pain that you would expect to go away in a few days, such as:
  - pain after surgery
  - headache or migraine
  - dental pain
- You have an allergy to any of the ingredients in SUBSYS:
  - Active ingredient: fentanyl
  - Inactive ingredients: dehydrated alcohol 63.6%, purified water, propylene glycol, xylitol, and L-menthol.

Before taking SUBSYS, tell your healthcare provider if you have a history of:

- Trouble breathing or lung problems such as asthma, wheezing, or shortness of breath
- head injury, seizures
- liver, kidney, thyroid problems
- problems urinating
- pancreas or gallbladder problems
- abuse of street or prescription drugs, alcohol addiction
- mental problems including major depression, schizophrenia or hallucinations (seeing or hearing things that are not there)
- Slow heart rate or other heart problems
- Low blood pressure

Tell your healthcare provider if you are:

- Pregnant or planning to become pregnant. Prolonged use of SUBSYS during pregnancy can cause withdrawal symptoms in your newborn baby that could be life-threatening if not recognized and treated.
- Breastfeeding. SUBSYS passes into breast milk and may harm your baby.
- Taking prescription or over-the-counter medicines, vitamins, or herbal supplements. Taking SUBSYS with certain other medicines can cause serious side effects that could lead to death.

When taking SUBSYS:

- Do not change your dose. Take SUBSYS exactly as prescribed by your healthcare provider.
- See the detailed Instructions for Use for information about how to take SUBSYS.
- Use SUBSYS exactly as prescribed by your healthcare provider. Do not use more than 2 doses of SUBSYS for each episode of breakthrough cancer pain. You must wait four hours before treating a new episode of breakthrough pain with SUBSYS.
- Your healthcare provider will prescribe a starting dose of SUBSYS that may be different than other fentanyl containing medicines you may have been taking.
- Do not stop taking SUBSYS without talking to your healthcare provider.
- After you stop taking SUBSYS, see the “Instructions for Use” section at the end of this Medication Guide for information about the right way to dispose of SUBSYS when no longer needed.
- Dispose of expired, unwanted or unused SUBSYS by following the “Disposing of SUBSYS”directions in the Instructions for Use. Visit www.fda.gov/drugdisposal for additional information on disposalof unsed medicines.

- DO NOT drive or operate heavy machinery, until you know how SUBSYS affects you. SUBSYS can make you sleepy, dizzy, or lightheaded.
- DO NOT drink alcohol or use prescription or over-the-counter medicines that contain alcohol. Using products containing alcohol during treatment with SUBSYS may cause you to overdose and die.
- DO NOT Switch from SUBSYS to other medicines that contain fentanyl without talking with your healthcare provider. The amount of fentanyl in a dose of SUBSYS is not the same as the amount of fentanyl in other medicines that contain fentanyl.

The possible side effects of SUBSYS:

- Constipation, nausea, sleepiness, vomiting, tiredness, headache, dizziness, abdominal pain, weakness, anxiety, depression, rash, trouble sleeping, low red blood cell count, swelling of the arms, hands, legs, and feet. Call your healthcare provider if you have any of these symptoms and they are severe.
- Decreased blood pressure. This can make you feel dizzy or lightheaded if you get up too fast from sitting or lying down.

Get emergency medical help if you have:

- trouble breathing, shortness of breath, fast heartbeat, chest pain, swelling of your face, tongue, or throat, extreme drowsiness, light-headedness when changing positions, feeling faint, agitation, high body temperature, trouble walking, stiff muscles, or mental changes such as confusion.

These are not all the possible side effects of SUBSYS. Call your doctor for medical advice about side effects. You may report side effects to FDA at 1-800-FDA-1088. For more information go to dailymed.nlm.nih.gov.

Manufactured by: Renaissance Lakewood, LLC, Lakewood, NJ 08701

Distributed by: West Therapeutic Development, LLC, Northbrook, IL, 60062, (1-844-452-9263)

This Medication Guide has been approved by the U.S. Food and Drug Administration.

Issued: 02/2020

Child Safety Kit

The SUBSYS Child Safety Kit contains important information on the storage and handling of SUBSYS.

The SUBSYS Child Safety Kit includes:

- a portable pouch (FIGURE A) and lock (FIGURE B) for you to keep a small supply of SUBSYS. Keep the rest of your SUBSYS in the locked storage space.
  Figure A
  Figure B
- a package of cabinet and drawer child safety latches (FIGURE C) to secure the storage space where SUBSYS is kept at home.
  Figure C
- Keep the pouch locked and away from children. (See FIGURE C)

Instructions for Use

Before you use SUBSYS, it is important that you read the Medication Guide and these Instructions for Use. Be sure that you read, understand, and follow these Instructions for Use so that you use SUBSYS the right way. Ask your healthcare provider or pharmacist if you have questions about the right way to use SUBSYS.

What will I find in the SUBSYS package?
Each SUBSYS Carton contains (See Figure D) :

- individual blister packages containing spray units of SUBSYS
- a supply of small white disposal bags for use when disposing of used SUBSYS units and charcoal-lined disposal pouches
- a supply of charcoal-lined disposal pouches (wrapped in aluminum foil) for use when disposing of the contents of unused SUBSYS units
  - Call West Therapeutic Development, LLC at 1-844-452-9263 for additional supplies of disposal bags and charcoal-lined disposal pouches.
- a Medication Guide (not shown)
- a Package Insert (not shown)

- When you get an episode of breakthrough cancer pain, take the dose prescribed by your healthcare provider as follows: SUBSYS comes in individual blister packages. Do not open the blister package until you are ready to use it.
  Figure D
- Remove the SUBSYS spray unit from the blister package by cutting the dashed line with a pair of scissors. (See Figure E.)
  Figure E
- To correctly use SUBSYS:
  - Swallow any saliva in your mouth
  - Hold the SUBSYS spray unit upright using your index and middle fingers and thumb. (See Figure F.)
    Figure F
  - Point the nozzle into your mouth and under your tongue. (See Figures G and H)
    Figure G
    Figure H
  - Squeeze your fingers and thumb together to spray SUBSYS under your tongue. (See Figure I)
  - Hold the medicine under your tongue for 30-60 seconds. Do not spit out any medicine. Do not rinse your mouth.
    Figure I
  - The SUBSYS spray unit will remain locked after use. (See Figure J)
    Figure J

Disposing of SUBSYS:

After using SUBSYS, dispose of the spray unit as follows:

- Place the used SUBSYS spray unit into one of the disposal bags provided in the carton containing the spray units. (See Figure K)
  Figure K
- Remove the backing from the adhesive strip.
- Fold the flap to seal the bag. (See Figure L)
  Figure L
- Discard in the trash out of the reach of children. (See Figure M)
  Figure M

Do not ingest the contents of the bag.

Disposal of any unused SUBSYS when no longer needed:

Before you throw away the SUBSYS spray units, you must empty all of the medicine into the charcoal-lined disposal pouch. This protects others, especially children from harm . Charcoal-lined disposal pouches are supplied wrapped in an aluminum foil package.

- Remove a charcoal-lined disposal pouch from the aluminum foil package by tearing open the package at the notch. (See Figures N)
  Figure N

- Remove the SUBSYS spray unit from the blister package by cutting the dashed line with a pair of scissors. (See Figure O)
  Figure O

- Hold the charcoal-lined disposal pouch with the opening facing up. Put the nozzle of the SUBSYS spray unit upside-down into the opening of the charcoal-lined disposal pouch. (See Figure P)
  Figure P

- Squeeze your fingers and thumb together to spray SUBSYS into the charcoal-lined disposal pouch.
- Dispose of the spray unit in a disposal bag. (See Figures K and L)
- Repeat steps O and P for each unused SUBSYS spray unit. The charcoal-lined disposal pouch may be used for disposing of the contents of up to 10 spray units.
- Make sure all unused spray units have been sprayed into a charcoal-lined disposal pouch.
  To seal a used charcoal-lined disposal pouch, remove the backing from the adhesive strip. (See Figure Q) Fold the flap down and press to seal the charcoal-lined disposal pouch.
  Figure Q

- Place the sealed charcoal-lined disposal pouch into a disposal bag. (See Figure R)
  Figure R

- To seal the disposal bag, remove the backing from the adhesive strip. Fold the flap down and press to seal.
- Discard the sealed disposal bag in the trash out of the reach of children. (See Figure S)
  Figure S

- Do not ingest the contents of the bag.

If you need help with disposal of SUBSYS, call Insys Therapeutics, Inc. at 1-877-978-2797 or call your local Drug Enforcement Agency (DEA) office.

This Medication Guide has been approved by the U.S. Food and Drug Administration.

Manufactured by:
Renaissance Lakewood, LLC, Lakewood, NJ 08701

for:
West Therapeutic Development, LLC, Northbrook, IL 60062

Revised February 2020

SUB-MKT-19-005(a)
022020